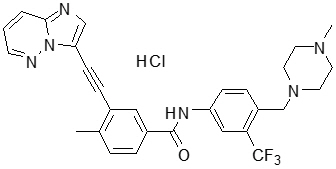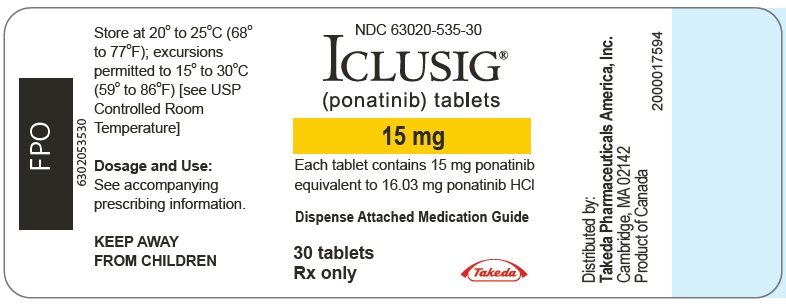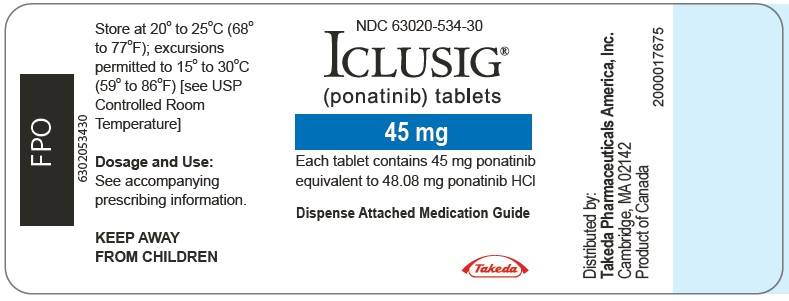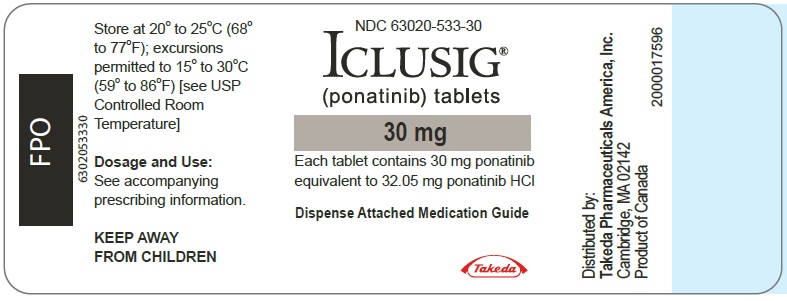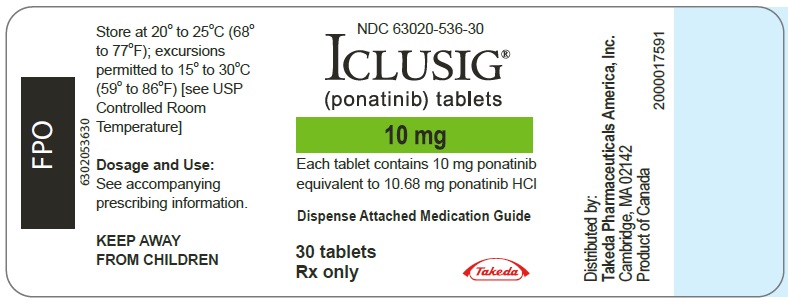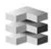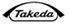 DRUG LABEL: Iclusig
NDC: 63020-535 | Form: TABLET, FILM COATED
Manufacturer: Takeda Pharmaceuticals America, Inc.
Category: prescription | Type: HUMAN PRESCRIPTION DRUG LABEL
Date: 20251016

ACTIVE INGREDIENTS: ponatinib hydrochloride 15 mg/1 1
INACTIVE INGREDIENTS: lactose monohydrate; microcrystalline cellulose; sodium starch glycolate type B potato; silicon dioxide; magnesium stearate

HIGHLIGHTS OF PRESCRIBING INFORMATION

These highlights do not include all the information needed to use ICLUSIG safely and effectively. See full prescribing information for ICLUSIG.
ICLUSIG® (ponatinib) tablets, for oral use
Initial U.S. Approval: 2012

RECENT MAJOR CHANGES

Warnings and Precautions (5) | 10/2025

WARNING: ARTERIAL OCCLUSIVE EVENTS, VENOUS THROMBOEMBOLIC EVENTS, HEART FAILURE, and HEPATOTOXICITY

See full prescribing information for complete boxed warning.

- Arterial occlusive events (AOEs), including fatalities, have occurred in ICLUSIG-treated patients. AOEs included fatal myocardial infarction, stroke, stenosis of large arterial vessels of the brain, severe peripheral vascular disease, and the need for urgent revascularization procedures. Patients with and without cardiovascular risk factors, including patients age 50 years or younger, experienced these events. Monitor for evidence of AOEs. Interrupt or discontinue ICLUSIG based on severity. Consider benefit-risk to guide a decision to restart ICLUSIG. (2.2, 5.1)
- Venous thromboembolic events (VTEs) have occurred in ICLUSIG-treated patients. Monitor for evidence of VTEs. Interrupt or discontinue ICLUSIG based on severity. (2.2, 5.2)
- Heart failure, including fatalities, occurred in ICLUSIG-treated patients. Monitor for heart failure and manage patients as clinically indicated. Interrupt or discontinue ICLUSIG for new or worsening heart failure. (2.2, 5.3)
- Hepatotoxicity, liver failure and death have occurred in ICLUSIG-treated patients. Monitor liver function tests. Interrupt or discontinue ICLUSIG based on severity. (2.2, 5.4)

1 INDICATIONS AND USAGE

ICLUSIG is a kinase inhibitor indicated for the treatment of adult patients with:

Philadelphia Chromosome-Positive Acute Lymphoblastic Leukemia (Ph+ ALL)

- Newly diagnosed Ph+ ALL, in combination with chemotherapy.
  This indication is approved under accelerated approval based on minimal residual disease (MRD)-negative complete remission (CR) at the end of induction. Continued approval for this indication may be contingent upon verification of clinical benefit in a confirmatory trial(s). (1)
- As monotherapy in Ph+ ALL for whom no other kinase inhibitors are indicated or T315I-positive Ph+ ALL. (1)

Chronic Myeloid Leukemia (CML)

- Chronic phase (CP) CML with resistance or intolerance to at least two prior kinase inhibitors. (1)
- Accelerated phase (AP) or blast phase (BP) CML for whom no other kinase inhibitors are indicated. (1)
- T315I-positive CML (chronic phase, accelerated phase, or blast phase). (1)

Limitations of Use: ICLUSIG is not indicated and is not recommended for the treatment of patients with newly diagnosed CP-CML. (5.7)

2 DOSAGE AND ADMINISTRATION

- Recommended Dosage in Newly Diagnosed Ph+ ALL: Starting dose is 30 mg orally once daily in combination with chemotherapy, with a reduction to 15 mg once daily upon achievement of MRD-negative (≤0.01% BCR::ABL1/ABL1) CR at the end of induction. (2.1)
- Recommended Dosage in Monotherapy for Ph+ ALL for Whom No Other Kinase Inhibitors are Indicated or T315I-positive Ph+ ALL: Starting dose is 45 mg orally once daily. (2.1)
- Recommended Dosage in CP-CML: Starting dose is 45 mg orally once daily with a reduction to 15 mg once daily upon achievement of ≤1% BCR::ABL1IS. (2.1)
- Recommended Dosage in AP-CML and BP-CML: Starting dose is 45 mg orally once daily. (2.1)
- Hepatic Impairment: See the Full Prescribing Information for dosage modifications for hepatic impairment. (2.4)
- ICLUSIG may be taken with or without food. (2.1)

3 DOSAGE FORMS AND STRENGTHS

Tablets: 10 mg, 15 mg, 30 mg, and 45 mg. (3)

4 CONTRAINDICATIONS

None. (4)

5 WARNINGS AND PRECAUTIONS

- Hypertension: Monitor blood pressure and manage hypertension as clinically indicated. Interrupt, dose reduce or stop ICLUSIG if hypertension is not medically controlled. (2.2, 5.5)
- Pancreatitis: Monitor serum lipase. Interrupt, then resume at the same or reduced dose or discontinue ICLUSIG based on severity. Evaluate for pancreatitis when lipase elevation is accompanied by abdominal symptoms. (2.2, 5.6)
- Neuropathy: Monitor for symptoms of peripheral and cranial neuropathy. Interrupt, then resume at the same or reduced dose or discontinue ICLUSIG based on recurrence/severity. (2.2, 5.8)
- Ocular Toxicity: Conduct comprehensive eye exams at baseline and periodically during treatment. (5.9)
- Hemorrhage: Monitor for hemorrhage and manage patients as clinically indicated. Interrupt, then resume at the same or reduced dose or discontinue ICLUSIG based on recurrence/severity. (2.2, 5.10)
- Fluid Retention: Monitor for fluid retention and manage patients as clinically indicated. Interrupt, then resume at the same or reduced dose or discontinue ICLUSIG based on recurrence/severity. (2.2, 5.11)
- Cardiac Arrhythmias: Monitor for signs or symptoms of arrhythmias and manage patients as clinically indicated. Interrupt, then resume at the same or reduced dose or discontinue ICLUSIG based on recurrence/severity. (5.12)
- Myelosuppression: Obtain complete blood counts every 2 weeks for the first 3 months and then monthly or as clinically indicated. If ANC less than 1 × 10^9/L or platelets less than 50 × 10^9/L, interrupt ICLUSIG until ANC at least 1.5 × 10^9/L and platelets at least 75 × 10^9/L, then resume at same or reduced dose. (2.2, 5.13)
- Tumor Lysis Syndrome: Ensure adequate hydration and correct elevated uric acid levels prior to initiating ICLUSIG. (5.14)
- Reversible Posterior Leukoencephalopathy Syndrome (RPLS): Interrupt ICLUSIG until resolution. The safety of resumption of ICLUSIG in patients upon resolution of RPLS is unknown. (5.15)
- Impaired Wound Healing and Gastrointestinal Perforation: Withhold ICLUSIG for at least 1 week prior to elective surgery. Do not administer for at least 2 weeks following major surgery and until adequate wound healing. The safety of resumption of ICLUSIG after resolution of wound healing complications has not been established. (5.16)
- Embryo-Fetal Toxicity: Can cause fetal harm. Advise females of reproductive potential of the potential risk to a fetus and to use effective contraception. (5.17, 8.1, 8.3)

6 ADVERSE REACTIONS

Most common adverse reactions (occurring in >20% of patients) are:

- ICLUSIG as a single agent: rash and related conditions, arthralgia, abdominal pain, fatigue, headache, constipation, hypertension, dry skin, hepatotoxicity, fluid retention and edema, pyrexia, pancreatitis/lipase elevation, nausea, hemorrhage, anemia, AOEs, and cardiac arrhythmias. The most common Grade 3 or 4 laboratory abnormalities (>20%) are platelet count decreased, neutrophil cell count decreased, and white blood cell decreased. (6.1)
- ICLUSIG in combination with chemotherapy: hepatotoxicity, arthralgia, rash and related conditions, headache, pyrexia, abdominal pain, constipation, fatigue, nausea, oral mucositis, hypertension, pancreatitis/lipase elevation, neuropathy peripheral, hemorrhage, febrile neutropenia, fluid retention and edema, vomiting, paresthesia, and cardiac arrhythmias. The most common Grade 3 or 4 laboratory abnormalities (>20%) are decreased white blood cell count, decreased neutrophil cell count, decreased platelet count, decreased lymphocyte cell count, decreased hemoglobin, increased lipase, and increased alanine aminotransferase. (6.1)

To report SUSPECTED ADVERSE REACTIONS, contact Takeda Pharmaceuticals at 1-844-817-6468 or FDA at 1-800-FDA-1088 or www.fda.gov/medwatch.

7 DRUG INTERACTIONS

- Strong CYP3A Inhibitors: Avoid coadministration or reduce ICLUSIG dose if coadministration cannot be avoided. (2.3, 7.1)
- Strong CYP3A Inducers: Avoid coadministration. (7.1)

8 USE IN SPECIFIC POPULATIONS

Lactation: Advise not to breastfeed. (8.2)

FULL PRESCRIBING INFORMATION

WARNING: ARTERIAL OCCLUSIVE EVENTS, VENOUS THROMBOEMBOLIC EVENTS, HEART FAILURE, and HEPATOTOXICITY

Arterial Occlusive Events:

- Arterial occlusive events (AOEs), including fatalities, have occurred in ICLUSIG-treated patients. AOEs included fatal myocardial infarction, stroke, stenosis of large arterial vessels of the brain, severe peripheral vascular disease, and the need for urgent revascularization procedures. Patients with and without cardiovascular risk factors, including patients age 50 years or younger, experienced these events. Monitor for evidence of AOEs. Interrupt or discontinue ICLUSIG based on severity. Consider benefit-risk to guide a decision to restart ICLUSIG [see Dosage and Administration (2.2), Warnings and Precautions (5.1)].

Venous Thromboembolic Events:

- Venous thromboembolic events (VTEs) have occurred in ICLUSIG-treated patients. Monitor for evidence of VTEs. Interrupt or discontinue ICLUSIG based on severity [see Dosage and Administration (2.2), Warnings and Precautions (5.2)].

Heart Failure:

- Heart failure, including fatalities, occurred in ICLUSIG-treated patients. Monitor for heart failure and manage patients as clinically indicated. Interrupt or discontinue ICLUSIG for new or worsening heart failure [see Dosage and Administration (2.2), Warnings and Precautions (5.3)].

Hepatotoxicity:

- Hepatotoxicity, liver failure and death have occurred in ICLUSIG-treated patients. Monitor liver function tests. Interrupt or discontinue ICLUSIG based on severity [see Dosage and Administration (2.2), Warnings and Precautions (5.4)].

1 INDICATIONS AND USAGE

ICLUSIG® is indicated for the treatment of adult patients with:

Philadelphia Chromosome-Positive Acute Lymphoblastic Leukemia (Ph+ ALL)

- Newly diagnosed Ph+ ALL in combination with chemotherapy.
  This indication is approved under accelerated approval based on minimal residual disease (MRD)-negative complete remission (CR) at the end of induction [see Clinical Studies (14)]. Continued approval for this indication may be contingent upon verification of clinical benefit in a confirmatory trial(s).
- As monotherapy in Ph+ ALL for whom no other kinase inhibitors are indicated or T315I-positive Ph+ ALL.

Chronic Myeloid Leukemia (CML)

- Chronic phase (CP) CML with resistance or intolerance to at least two prior kinase inhibitors.
- Accelerated phase (AP) or blast phase (BP) CML for whom no other kinase inhibitors are indicated.
- T315I-positive CML (chronic phase, accelerated phase, or blast phase).

Limitations of Use: ICLUSIG is not indicated and is not recommended for the treatment of patients with newly diagnosed CP-CML [see Warnings and Precautions (5.7)].

2 DOSAGE AND ADMINISTRATION

2.1 Recommended Dosage

Newly Diagnosed Ph+ ALL

The recommended starting dosage of ICLUSIG in combination with chemotherapy is 30 mg orally once daily with a reduction to 15 mg orally once daily upon achievement of MRD-negative (≤0.01% BCR::ABL1/ABL1) CR at the end of induction. Continue ICLUSIG in combination with chemotherapy for up to 20 cycles until loss of response or unacceptable toxicity [see Clinical Studies (14)].

For a description of dosing of agents administered in combination with ICLUSIG, [see Clinical Studies (14)].

Monotherapy for Ph+ ALL for Whom No Other Kinase Inhibitors Are Indicated or T315I-positive Ph+ ALL

The optimal dose of ICLUSIG has not been identified.

The recommended starting dosage of ICLUSIG is 45 mg orally once daily. Continue ICLUSIG until loss of response or unacceptable toxicity.

Consider discontinuing ICLUSIG if response has not occurred by 3 months.

CP-CML

The recommended starting dosage of ICLUSIG is 45 mg orally once daily with a reduction to 15 mg orally once daily upon achievement of ≤1% BCR::ABL1IS. Patients with loss of response can re-escalate the dose of ICLUSIG to a previously tolerated dosage of 30 mg or 45 mg orally once daily. Continue ICLUSIG until loss of response at the re-escalated dose or unacceptable toxicity.

Consider discontinuing ICLUSIG if hematologic response has not occurred by 3 months.

AP-CML and BP-CML

The optimal dose of ICLUSIG has not been identified.

The recommended starting dosage of ICLUSIG is 45 mg orally once daily. Consider reducing the dose of ICLUSIG for patients with accelerated phase (AP) CML who have achieved a major cytogenetic response. Continue ICLUSIG until loss of response or unacceptable toxicity.

Consider discontinuing ICLUSIG if response has not occurred by 3 months.

Administration

Advise patients of the following:

- ICLUSIG may be taken with or without food.
- Swallow tablets whole. Do not crush, break, cut or chew tablets.
- If a dose is missed, take the next dose at the regularly scheduled time the next day.

2.2 Dosage Modifications for Adverse Reactions

Recommended dosage modifications of ICLUSIG for adverse reactions are provided in Table 1 and recommended dose reductions of ICLUSIG for adverse reactions are presented in Table 2.

Table 1: Recommended Dosage Modifications for ICLUSIG for Adverse Reactions
Adverse Reaction | Severity | ICLUSIG Dosage Modifications
AOE: cardiovascular or cerebrovascular [see Warnings and Precautions (5.1)] | Grade 1 | Interrupt ICLUSIG until resolved, then resume at same dose.
AOE: cardiovascular or cerebrovascular [see Warnings and Precautions (5.1)] | Grade 2 | Interrupt ICLUSIG until Grade 0 or 1, then resume at next lower dose. Discontinue ICLUSIG if recurrence.
AOE: cardiovascular or cerebrovascular [see Warnings and Precautions (5.1)] | Grade 3 or 4 | Discontinue ICLUSIG.
AOE: peripheral vascular and other or VTE [see Warnings and Precautions (5.1, 5.2)] | Grade 1 | Interrupt ICLUSIG until resolved, then resume at same dose.
AOE: peripheral vascular and other or VTE [see Warnings and Precautions (5.1, 5.2)] | Grade 2 | Interrupt ICLUSIG until Grade 0 or 1, then resume at same dose. If recurrence, interrupt ICLUSIG until Grade 0 or 1, then resume at next lower dose.
AOE: peripheral vascular and other or VTE [see Warnings and Precautions (5.1, 5.2)] | Grade 3 | Interrupt ICLUSIG until Grade 0 or 1, then resume at next lower dose. Discontinue ICLUSIG if recurrence.
AOE: peripheral vascular and other or VTE [see Warnings and Precautions (5.1, 5.2)] | Grade 4 | Discontinue ICLUSIG.
Heart Failure [see Warnings and Precautions (5.3)] | Grade 2 or 3 | Interrupt ICLUSIG until Grade 0 or 1, then resume at next lower dose. Discontinue ICLUSIG if recurrence.
Heart Failure [see Warnings and Precautions (5.3)] | Grade 4 | Discontinue ICLUSIG.
Hepatotoxicity [see Warnings and Precautions (5.4)] | AST or ALT greater than 3 times ULN | Interrupt ICLUSIG until Grade 0 or 1, then resume at next lower dose.
Hepatotoxicity [see Warnings and Precautions (5.4)] | AST or ALT at least 3 times ULN concurrent with bilirubin greater than 2 times ULN and alkaline phosphatase less than 2 times ULN | Discontinue ICLUSIG.
Pancreatitis and Elevated Lipase [see Warnings and Precautions (5.6)] | Serum lipase greater than 1 to 1.5 times ULN | Consider interrupting ICLUSIG until resolution, then resume at same dose.
Pancreatitis and Elevated Lipase [see Warnings and Precautions (5.6)] | Serum lipase greater than 1.5 to 2 times ULN, 2 to 5 times ULN and asymptomatic, or asymptomatic radiologic pancreatitis | Interrupt ICLUSIG until Grade 0 or 1 (less than 1.5 times ULN), then resume at next lower dose.
Pancreatitis and Elevated Lipase [see Warnings and Precautions (5.6)] | Serum lipase greater than 2 to 5 times ULN and symptomatic, symptomatic Grade 3 pancreatitis, or serum lipase greater than 5 times ULN and asymptomatic | Interrupt ICLUSIG until complete resolution of symptoms and after recovery of lipase elevation Grade 0 or 1, then resume at next lower dose.
Pancreatitis and Elevated Lipase [see Warnings and Precautions (5.6)] | Symptomatic pancreatitis and serum lipase greater than 5 times ULN | Discontinue ICLUSIG.
Myelosuppression [see Warnings and Precautions (5.13)] | ANC less than 1 × 10^9/L or Platelets less than 50 × 10^9/L | Interrupt ICLUSIG until ANC at least 1.5 × 10^9/L and platelet at least 75 × 10^9/L, then resume at same dose. If recurrence, interrupt ICLUSIG until resolution, then resume at next lower dose.
Other Non-hematologic Adverse Reactions [see Warnings and Precautions (5.5, 5.8, 5.10, 5.11, 5.12)] | Grade 1 | Interrupt ICLUSIG until resolved, then resume at same dose.
Other Non-hematologic Adverse Reactions [see Warnings and Precautions (5.5, 5.8, 5.10, 5.11, 5.12)] | Grade 2 | Interrupt ICLUSIG until Grade 0 or 1, then resume at same dose. If recurrence, interrupt ICLUSIG until Grade 0 or 1, then resume at next lower dose.
Other Non-hematologic Adverse Reactions [see Warnings and Precautions (5.5, 5.8, 5.10, 5.11, 5.12)] | Grade 3 or 4 | Interrupt ICLUSIG until Grade 0 or 1, then resume at next lower dose. Discontinue ICLUSIG if recurrence.
Based on CTCAE v5.0: Grade 1 mild, Grade 2 moderate, Grade 3 severe, Grade 4 life-threatening
ULN = Upper Limit of Normal for the lab; AOE = Arterial Occlusive Event; VTE = Venous Thromboembolic Event; ANC = absolute neutrophil count

Table 2: Recommended Dose Reductions for ICLUSIG for Adverse Reactions
Dose Reduction | Dosage for Patients with CP-CML | Dosage for Patients with AP-CML, BP-CML, and Ph+ ALL Monotherapy | Dosage for Patients with Newly Diagnosed Ph+ ALL
First | 30 mg orally once daily | 30 mg orally once daily | 15 mg orally once daily
Second | 15 mg orally once daily | 15 mg orally once daily | 10 mg orally once daily
Third | 10 mg orally once daily | Permanently discontinue ICLUSIG in patients unable to tolerate 15 mg orally once daily. | Permanently discontinue ICLUSIG in patients unable to tolerate 10 mg orally once daily.
Subsequent Reduction | Permanently discontinue ICLUSIG in patients unable to tolerate 10 mg orally once daily. | Permanently discontinue ICLUSIG in patients unable to tolerate 15 mg orally once daily. | Permanently discontinue ICLUSIG in patients unable to tolerate 10 mg orally once daily.

2.3 Dosage Modification for Coadministration of Strong CYP3A Inhibitors

Avoid coadministration of ICLUSIG with strong CYP3A inhibitors. If coadministration of a strong CYP3A inhibitor cannot be avoided, reduce the dosage of ICLUSIG as recommended in Table 3.

After the strong CYP3A inhibitor has been discontinued for 3 to 5 elimination half-lives, resume the ICLUSIG dosage that was tolerated prior to initiating the strong CYP3A inhibitor [see Drug Interactions (7.1), Clinical Pharmacology (12.3)].

Table 3: Recommended ICLUSIG Dosage for Coadministration of Strong CYP3A Inhibitors
Current ICLUSIG Dosage | Recommended ICLUSIG Dosage with a Strong CYP3A Inhibitor
45 mg orally once daily | 30 mg orally once daily
30 mg orally once daily | 15 mg orally once daily
15 mg orally once daily | 10 mg orally once daily
10 mg orally once daily | Avoid coadministration of ICLUSIG with a strong CYP3A inhibitor

2.4 Dosage for Patients with Hepatic Impairment

For patients with CP-CML, AP-CML, BP-CML, and Ph+ ALL receiving monotherapy, reduce the starting dose of ICLUSIG from 45 mg orally once daily to 30 mg orally once daily in patients with pre-existing hepatic impairment (Child-Pugh A, B, or C).

For patients with newly diagnosed Ph+ ALL, no dosage adjustment is recommended when administering ICLUSIG to patients with mild hepatic impairment (Child-Pugh A). Closely monitor patients with moderate or severe hepatic impairment (Child-Pugh B or C) and modify the ICLUSIG dosage in the event of adverse reactions [see Dosage and Administration (2.2), Use in Specific Populations (8.6)].

3 DOSAGE FORMS AND STRENGTHS

Tablets, film-coated:

- 10 mg of ponatinib: Oval, white to off-white, biconvex, debossed "NZ" on one side and plain on the other side
- 15 mg of ponatinib: Round, white, biconvex, debossed "A5" on one side and plain on the other side
- 30 mg of ponatinib: Round, white, biconvex, debossed "C7" on one side and plain on the other side
- 45 mg of ponatinib: Round, white, biconvex, debossed "AP4" on one side and plain on the other side

4 CONTRAINDICATIONS

None.

5 WARNINGS AND PRECAUTIONS

5.1 Arterial Occlusive Events

Arterial occlusive events (AOEs), including fatalities, occurred in patients who received ICLUSIG [see Adverse Reactions (6.1)].

In PhALLCON, 6% of 163 patients experienced AOEs, of which 3.1%, 1.8%, and 1.2% experienced cardiovascular, cerebrovascular, and peripheral vascular AOEs, respectively. The median time to onset of the first AOE was 11.3 months (range: 8 days to 2.8 years). Grade 3 or 4 AOEs occurred in 3.7% of patients; the most frequent Grade 3 or 4 AOEs were myocardial infarction (1.2%), peripheral arterial occlusive disease (1.2%), angina pectoris and cerebrovascular accident (0.6% each). Fatal AOE of sudden death occurred in 1 patient (0.6%). AOEs were more frequent with increasing age [see Use in Specific Populations (8.5)].

In PhALLCON, patients with uncontrolled hypertension, hypertriglyceridemia, or diabetes were excluded. Patients with clinically significant, uncontrolled, or active cardiovascular disease, including any history of myocardial infarction, peripheral vascular infarction, revascularization procedure, venous thromboembolism, clinically significant atrial/ventricular tachyarrhythmias, unstable angina, or congestive heart failure within the 6 months prior to the first dose of ICLUSIG, were also excluded.

In OPTIC, of the 94 patients who received a starting dose of 45 mg (45 mg → 15 mg), 18% experienced AOEs, of which 11%, 4.3%, and 3.2% experienced cardiovascular, cerebrovascular or peripheral vascular AOEs, respectively. The median time to onset of the first cardiovascular, cerebrovascular, or peripheral vascular event was 9.4 months (range: 12 days to 5.7 years), 11.7 months (range: 15 days to 1.6 years), and 6.3 months (range: 23 days to 3.6 years), respectively. Grade 3 or 4 AOEs occurred in 7% of patients; the most frequent Grade 3 or 4 AOEs were myocardial infarction, acute coronary syndrome, arterial thrombosis, ischemic stroke, ischemic cerebral infarction, subclavian artery stenosis and unstable angina (1.1% each). Fatal AOEs occurred in 4 patients (4.3%); including sudden death (2.1%), myocardial ischemia (1.1%) and myocardial infarction (1.1%). AOEs were more frequent with increasing age [see Use in Specific Populations (8.5)].

In OPTIC, patients with uncontrolled hypertension or diabetes and patients with clinically significant, uncontrolled, or active cardiovascular disease, including any history of myocardial infarction, peripheral vascular infarction, revascularization procedure, congestive heart failure, venous thromboembolism, or clinically significant atrial/ventricular arrhythmias, were excluded.

In PACE, 26% of 449 patients experienced AOEs, of which 15%, 7%, and 11% experienced cardiovascular, cerebrovascular, and peripheral vascular AOEs, respectively. Some patients experienced recurrent or multisite vascular occlusion. The median time to onset of the first cardiovascular, cerebrovascular, and peripheral vascular AOEs was 1 year (range: 1 day to 4.1 years), 1.4 years (range: 2 days to 4.5 years), and 2 years (range: 10 days to 4.9 years), respectively. Grade 3 or 4 AOEs occurred in 14% of patients; the most frequent Grade 3 or 4 AOEs were peripheral arterial occlusive disease (3.1%), myocardial infarction (2%), coronary artery disease (1.6%), and cerebral infarction (1.6%). Fatal AOEs occurred in 9 patients (2%); the most frequent fatal AOE was cardiac arrest (0.9%).

In PACE, fatal and life-threatening AOEs occurred within 2 weeks of starting treatment at 45 mg, and at dose levels as low as 15 mg per day. Patients with and without cardiovascular risk factors, including patients age 50 years or younger, experienced AOEs. AOEs were more frequent with increasing age [see Use in Specific Populations (8.5)] and in patients with history of ischemia, hypertension, diabetes, or hypercholesterolemia. The most common risk factors in patients with AOEs were history of hypertension (67%; 77/115), hypercholesterolemia (59%; 68/115), and non-ischemic cardiac disease (43%; 49/115).

In PACE, patients developed heart failure concurrent or subsequent to a myocardial ischemic event [see Warnings and Precautions (5.3)]. Patients required revascularization procedures (coronary, cerebrovascular, and peripheral arterial). ICLUSIG caused stenosis over multiple segments in major arterial vessels that supply the brain (e.g., carotid, vertebral, middle cerebral artery). Patients developed digital or distal extremity necrosis and required amputations. Renal artery stenosis associated with worsening, labile or treatment-resistant hypertension occurred in some ICLUSIG-treated patients [see Warnings and Precautions (5.5)].

In PACE, patients with uncontrolled hypertriglyceridemia and patients with clinically significant or active cardiovascular disease, including any history of clinically significant atrial/ventricular arrhythmias or history of myocardial infarction, unstable angina, or congestive heart failure within the 3 months prior to the first dose of ICLUSIG, were excluded [see Adverse Reactions (6.1)]. Consider whether the benefits of ICLUSIG are expected to exceed the risks.

Monitor for evidence of AOEs. Interrupt, then resume at the same or decreased dose or discontinue ICLUSIG based on recurrence/severity [see Dosage and Administration (2.2)]. Consider benefit-risk to guide a decision to restart ICLUSIG.

5.2 Venous Thromboembolic Events

Serious or severe VTEs have occurred in patients who received ICLUSIG.

In PhALLCON, VTEs occurred in 12% of 163 patients, including serious or severe (Grade 3 or 4) in 3.1%. VTEs included deep vein thrombosis (6%), superficial vein thrombosis (2.5%), embolism (1.8%), pulmonary embolism and thrombosis (1.2% each), and jugular vein thrombosis and retinal vein occlusion (0.6% each). The median time to onset of the first VTE event was 2.5 months (range: 6 days to 1.8 years).

In OPTIC, of the 94 patients who received a starting dose of 45 mg, 2 patients experienced a VTE (Grade 1 retinal vein occlusion and grade 2 phlebitis).

In PACE, VTEs occurred in 6% of 449 patients, including serious or severe (Grade 3 or 4) in 5.8%. VTEs included deep venous thrombosis (2.2%), pulmonary embolism (1.8%), superficial thrombophlebitis (0.7%), retinal vein occlusion (0.7%), and retinal vein thrombosis (0.4%) with vision loss. VTEs occurred in 10% of the 62 patients with BP-CML, 9% of the 32 patients with Ph+ ALL, 6% of the 270 patients with CP-CML, and 3.5% of the 85 patients with AP-CML.

Monitor for evidence of VTEs. Interrupt, then resume at the same or decreased dose or discontinue ICLUSIG based on recurrence/severity [see Dosage and Administration (2.2)].

5.3 Heart Failure

Fatal, serious or severe heart failure events have occurred in patients who received ICLUSIG.

In PhALLCON, heart failure occurred in 6% of 163 patients; 1.2% experienced serious or severe (Grade 3 or 4) heart failure. The most frequently reported heart failure event (>1 patient) was increased brain natriuretic peptide (BNP) (2.5%).

In OPTIC, of the 94 patients who received a starting dose of 45 mg, heart failure occurred in 20% of patients; 2.1% experienced serious or severe (Grade 3 or 4) heart failure. The most frequently reported heart failure events (>1 patient each) were left ventricular hypertrophy (5%), left ventricular dysfunction (5%), BNP increased (5%), cardiac failure (3.2%), left atrial dilatation (2.1%) and ejection fraction decreased (2.1%).

Fatal or serious heart failure occurred in PACE. Heart failure occurred in 9% of 449 patients; 7% experienced serious or severe (Grade 3 or higher) heart failure. The most frequently reported heart failure events (≥2%) were congestive cardiac failure (3.1%), decreased ejection fraction (2.9%), and cardiac failure (2%).

Monitor patients for signs or symptoms consistent with heart failure and manage heart failure as clinically indicated. Interrupt, then resume at reduced dose or discontinue ICLUSIG for new or worsening heart failure [see Dosage and Administration (2.2)].

5.4 Hepatotoxicity

ICLUSIG can cause hepatotoxicity, including liver failure and death. Fulminant hepatic failure leading to death occurred in 3 patients, with hepatic failure occurring within 1 week of starting ICLUSIG in one of these patients. These fatal cases occurred in patients with BP-CML or Ph+ ALL treated with monotherapy.

In PhALLCON, hepatotoxicity occurred in 66% of 163 patients; 30% experienced Grade 3 or 4 hepatotoxicity. The median time to onset of hepatotoxicity was 15 days (range: 1 day to 10 months). The most frequent hepatotoxic events were elevated alanine aminotransferase (ALT), aspartate aminotransferase (AST), gamma-glutamyl transferase (GGT), bilirubin and alkaline phosphatase, decreased albumin and decreased blood fibrinogen. In 6% of the 73 patients who reported ALT or AST elevation, the elevations were not resolved by the date of the last follow-up.

In OPTIC, of the 94 patients who received a starting dose of 45 mg, hepatotoxicity occurred in 34% of patients; 7% experienced Grade 3 or 4 hepatotoxicity. The median time to onset of hepatotoxicity was 4.1 months, with a range of 1 day to 4.8 years. The most frequent hepatotoxic events were elevations of ALT, AST, alkaline phosphatase, and GGT. In one of the 26 patients who reported ALT or AST elevation, the event was not resolved by the date of last follow-up.

In PACE, hepatotoxicity occurred in 32% of 449 patients; 13% experienced Grade 3 or 4 hepatotoxicity. The median time to onset of hepatotoxicity was 3.1 months, with a range of 1 day to 4.9 years. The most frequent hepatotoxic events were elevations of ALT, AST, GGT, bilirubin, and alkaline phosphatase. In 9% of the 88 patients who reported ALT or AST elevation, the event was not resolved by the date of last follow-up.

Monitor liver function tests at baseline, then at least monthly or as clinically indicated. Interrupt, then resume at reduced dose or discontinue ICLUSIG based on recurrence/severity [see Dosage and Administration (2.2)].

5.5 Hypertension

Serious or severe hypertension, including hypertensive crisis, has occurred in patients who received ICLUSIG.

In PhALLCON, hypertension occurred in 34% of 163 patients; 14% experienced serious or severe hypertension. Based on vital signs data, Grade 1 blood pressure elevation occurred in 15 out of 60 (25%) patients with normal initial blood pressure, Grade 2 occurred in 67 out of 134 (50%) patients with initial blood pressure of less than Grade 2, and Grade 3 occurred in 63 out of 160 (39%) patients with an initial blood pressure of less than Grade 3.

In OPTIC, of the 94 patients who received a starting dose of 45 mg, hypertension events were reported in 37% of patients; 14% experienced serious or severe hypertension. Based on vital signs data, Grade 1 blood pressure elevation occurred in 8 out of 18 (44%) patients with normal initial blood pressure, Grade 2 occurred in 30 out of 81 (37%) patients with initial blood pressure of less than Grade 2, and Grade 3 occurred in 20 out of 92 (22%) patients with initial blood pressure of less than Grade 3. Three patients (3.2%) experienced hypertensive crisis.

In PACE, hypertension events were reported in 32% of 449 patients; 13% experienced serious or severe hypertension. Any post-baseline elevation of systolic or diastolic BP of Grade 2 or higher in patients with normal baseline blood pressure occurred in 44% of 449 patients. Grade 1 BP elevation occurred in 26%, Grade 2 in 45%, and Grade 3 in 26%. Two patients (<1%) experienced Grade 4 hypertension (hypertensive crisis).

Patients may require urgent clinical intervention for hypertension associated with confusion, headache, chest pain, or shortness of breath [see Adverse Reactions (6.1)]. Monitor blood pressure at baseline and as clinically indicated and manage hypertension as clinically indicated. Interrupt, dose reduce, or stop ICLUSIG if hypertension is not medically controlled [see Dosage and Administration (2.2)]. For significant worsening, labile or treatment-resistant hypertension, interrupt ICLUSIG and consider evaluating for renal artery stenosis.

5.6 Pancreatitis

Serious or severe pancreatitis has occurred in patients who received ICLUSIG.

In PhALLCON, pancreatitis occurred in 34% of 163 patients; 15% experienced serious or severe (Grade 3 or 4) pancreatitis. The median time to onset of pancreatitis was 8 days (range: 1 day to 2 years). In 7 patients with clinical pancreatitis that led to dose modification, pancreatitis resolved within 3 weeks. Laboratory abnormalities of amylase elevations occurred in 25% of patients, while lipase elevations occurred in 60% of patients.

In OPTIC, of the 94 patients who received a starting dose of 45 mg, pancreatitis occurred in 29% of patients; 16% experienced serious or severe (Grade 3 or 4) pancreatitis. Pancreatitis resulted in discontinuation in 1.1% of patients and interruption and/or dose reduction in 23% of patients. The median time to onset of pancreatitis was 1 month (range: 3 days to 4.1 years). In two patients with clinical pancreatitis that led to dose modification or treatment discontinuation, pancreatitis resolved within 2 weeks. Laboratory abnormalities of amylase elevation occurred in 15% of patients, while lipase elevation occurred in 40% of patients.

In PACE, pancreatitis occurred in 26% of 449 patients; 17% experienced serious or severe (Grade 3 or 4) pancreatitis. Pancreatitis resulted in discontinuation in 0.4% of patients and interruption and/or dose reduction in 17% of patients. The median time to onset of pancreatitis was 29 days (range: 1 day to 4 years). Nineteen of the 28 cases of clinical pancreatitis that led to dose modification or treatment discontinuation resolved within 2 weeks. Laboratory abnormalities of amylase elevations occurred in 18% of patients, while lipase elevations occurred in 39% of patients.

Monitor serum lipase every 2 weeks for the first 2 months and then monthly thereafter or as clinically indicated. Consider additional serum lipase monitoring in patients with a history of pancreatitis or alcohol abuse. Interrupt, then resume at the same or reduced dose or discontinue ICLUSIG based on severity [see Dosage and Administration (2.2)]. Evaluate for pancreatitis when lipase elevation is accompanied by abdominal symptoms.

5.7 Increased Toxicity in Newly Diagnosed Chronic Phase CML

In a prospective randomized clinical trial in the first line treatment of newly diagnosed patients with CP-CML, single agent ICLUSIG 45 mg once daily increased the risk of serious adverse reactions 2-fold compared to single agent imatinib 400 mg once daily. The median exposure to treatment was less than 6 months. The trial was halted for safety.

Arterial and venous thrombosis and occlusions occurred at least twice as frequently in the ICLUSIG arm compared to the imatinib arm. Compared to imatinib-treated patients, ICLUSIG-treated patients exhibited a greater incidence of myelosuppression, pancreatitis, hepatotoxicity, cardiac failure, hypertension, and skin and subcutaneous tissue disorders. ICLUSIG is not indicated and is not recommended for the treatment of patients with newly diagnosed CP-CML.

5.8 Neuropathy

In PhALLCON, peripheral neuropathy occurred in 68% of 163 patients; 3.1% experienced Grade 3 or 4 peripheral neuropathy. The most frequent peripheral neuropathies were neuropathy peripheral (33%), paresthesia (22%), and peripheral sensory neuropathy (12%). The median time to onset of peripheral neuropathy was 1.1 month (range: 1 day to 17.2 months). Cranial neuropathy was reported in 0.6% of 163 patients.

In OPTIC, of the 94 patients who received a starting dose of 45 mg, neuropathy occurred in 13% of patients. Peripheral neuropathy occurred in 11% of patients. The most frequently reported peripheral neuropathies were muscular weakness (3.2%), paresthesia (3.2%), hypoesthesia (2.1%) and neuropathy peripheral (2.1%). Cranial neuropathy developed in 2 patients. The median time to onset of peripheral neuropathy and cranial neuropathy was 1.1 years (range: 1 month to 4.1 years) and 3 years (range: 10.3 months to 5.2 years), respectively.

In PACE, neuropathy occurred in 22% of patients; 2.4% experienced Grade 3 or 4 neuropathy. Peripheral neuropathy occurred in 20% of 449 patients; 1.8% experienced Grade 3 or 4 peripheral neuropathy. The most frequent peripheral neuropathies were paresthesia (5%), neuropathy peripheral (4.5%), and hypoesthesia (3.6%). Cranial neuropathy developed in 3% of patients; 0.7% were Grade 3 or 4. The median time to onset of peripheral neuropathy and cranial neuropathy was 5.3 months (range: 1 day to 4.6 years) and 1.2 years (range: 18 days to 4 years), respectively.

Monitor patients for symptoms of neuropathy, such as hypoesthesia, hyperesthesia, paresthesia, discomfort, a burning sensation, neuropathic pain or weakness. Interrupt, then resume at the same or reduced dose or discontinue ICLUSIG based on recurrence/severity [see Dosage and Administration (2.2)].

5.9 Ocular Toxicity

Serious ocular toxicities leading to blindness or blurred vision have occurred in ICLUSIG-treated patients.

In PhALLCON, ocular toxicities occurred in 33% of 163 patients; 1.8% experienced a serious or severe ocular toxicity. The most frequent ocular toxicities were blurred vision and dry eye. Retinal toxicities occurred in 4.3% of patients; 0.6% experienced a Grade 3 retinal vein occlusion. The most frequent retinal toxicity event (>1 patient) was retinal hemorrhage (1.8%).

In OPTIC, of the 94 patients who received a starting dose of 45 mg, ocular toxicities occurred in 15% of patients; 1.1% experienced a serious or severe ocular toxicity. The most frequent ocular toxicities were dry eye, blurred vision and eye pain. Retinal toxicities occurred in 4.3% of patients, including age-related macular degeneration, arteriosclerotic retinopathy, retinal vascular disorder and retinal vein occlusion (1.1% each).

In PACE, ocular toxicities occurred in 30% of 449 patients; 3.6% experienced a serious or severe ocular toxicity. The most frequent ocular toxicities were dry eye, blurred vision, and eye pain. Retinal toxicities occurred in 3.6% of patients. The most frequent retinal toxicities were macular edema, retinal vein occlusion, retinal hemorrhage, and vitreous floaters (0.7% each).

Conduct comprehensive eye exams at baseline and periodically during treatment.

5.10 Hemorrhage

Fatal and serious hemorrhage events have occurred in patients who received ICLUSIG.

In PhALLCON, hemorrhage occurred in 31% of 163 patients; 2.5% experienced a serious hemorrhage. Intracranial hemorrhage was the most frequently reported serious hemorrhage, occurring in 1.2% of patients.

In OPTIC, of the 94 patients who received a starting dose of 45 mg, hemorrhage occurred in 13% of patients; 1 patient experienced a serious subdural hematoma.

In PACE, hemorrhage occurred in 28% of 449 patients; 6% experienced a serious hemorrhage and 1.3% experienced a fatal hemorrhage. The incidence of serious bleeding events was higher in patients with AP-CML, BP-CML, and Ph+ ALL. Gastrointestinal hemorrhage and subdural hematoma were the most frequently reported serious hemorrhages, each occurring in 0.9% of patients. Most hemorrhages occurred in patients with Grade 4 thrombocytopenia [see Warnings and Precautions (5.13)].

Monitor for hemorrhage and manage patients as clinically indicated. Interrupt, then resume at the same or reduced dose or discontinue ICLUSIG based on recurrence/severity [see Dosage and Administration (2.2)].

5.11 Fluid Retention

Fatal and serious fluid retention events have occurred in patients who received ICLUSIG.

In PhALLCON, fluid retention occurred in 24% of 163 patients; 1.2% experienced serious fluid retention, including pericardial effusion (1.2%). The most frequent occurrences of fluid retention were peripheral edema (11%) and pleural effusion (6%).

In OPTIC, of the 94 patients who received a starting dose of 45 mg, fluid retention occurred in 6% of patients. The most frequent fluid retention events were peripheral edema (3.2%), hydrothorax (2.1%) and pleural effusion (2.1%).

In PACE, fluid retention events occurred in 33% of 449 patients; 4.5% experienced serious fluid retention. One instance of brain edema was fatal. Serious fluid retention included pleural effusion (1.6%), pericardial effusion (1.6%), and angioedema (0.4%). The most frequent fluid retention events were peripheral edema (17%), pleural effusion (9%), pericardial effusion (4.2%) and peripheral swelling (3.8%).

Monitor for fluid retention and manage patients as clinically indicated. Interrupt, then resume at the same or reduced dose or discontinue ICLUSIG based on recurrence/severity [see Dosage and Administration (2.2)].

5.12 Cardiac Arrhythmias

In PhALLCON, cardiac arrhythmia events occurred in 22% of 163 patients; 2.5% experienced Grade 3 or 4 cardiac arrhythmias, including tachycardia, syncope, atrial fibrillation and supraventricular tachycardia (0.6%, each).

In OPTIC, of the 94 patients who received a starting dose of 45 mg, cardiac arrhythmias occurred in 27% of patients; 5% experienced Grade 3 or 4 cardiac arrhythmias including atrial fibrillation, cardio-respiratory arrest, supraventricular extrasystoles, supraventricular tachycardia and syncope (1.1%, each).

In PACE, cardiac arrhythmias occurred in 20% of 449 patients; 7% experienced Grade 3 or 4 cardiac arrhythmias. Ventricular arrhythmias occurred in 3.4% of the 89 patients who reported an arrhythmia, with one event being Grade 3 or 4. Symptomatic bradyarrhythmias that led to pacemaker implantation occurred in 1% of patients. Atrial fibrillation was the most frequent cardiac arrhythmia (8%), with 3.3% being Grade 3 or 4. Other Grade 3 or 4 arrhythmia events included syncope (2%), tachycardia and bradycardia (0.4% each), and QT interval prolongation, atrial flutter, sinus bradycardia, supraventricular tachycardia, ventricular tachycardia, atrial tachycardia, atrioventricular block complete, cardio-respiratory arrest, loss of consciousness, and sinus node dysfunction (0.2% each). For 31 patients, the arrythmia led to hospitalization.

Monitor for signs and symptoms suggestive of slow heart rate (fainting, dizziness) or rapid heart rate (chest pain, palpitations or dizziness) and manage patients as clinically indicated. Interrupt, then resume at the same or reduced dose or discontinue ICLUSIG based on recurrence/severity.

5.13 Myelosuppression

In PhALLCON, neutropenia occurred in 66% (Grade 3 or 4 occurred in 63%), thrombocytopenia occurred in 65% (Grade 3 or 4 occurred in 62%) and anemia occurred in 53% (Grade 3 or 4 occurred in 38%) of 163 patients. The median time to onset of Grade 3 or 4 myelosuppression was 27 days (range: 1 day to 9.2 months).

In OPTIC, of the 94 patients who received a starting dose of 45 mg, thrombocytopenia occurred in 66% (Grade 3 or 4 occurred in 31%), neutropenia occurred in 56% (Grade 3 or 4 occurred in 22%), and anemia occurred in 38% of patients (Grade 3 or 4 occurred in 14%). The median time to onset of Grade 3 or 4 myelosuppression was 1.3 months (range: 1 day to 1.2 years).

In PACE, neutropenia occurred in 56% (Grade 3 or 4 occurred in 34%), thrombocytopenia occurred in 63% (Grade 3 or 4 occurred in 40%), and anemia occurred in 52% of patients (Grade 3 or 4 occurred in 20%). The incidence of myelosuppression was greater in patients with AP-CML, BP-CML, and Ph+ ALL than in patients with CP-CML. Severe myelosuppression (Grade 3 or 4) was observed early in treatment, with a median onset time of 29 days (range: 1 day to 4.1 years).

Obtain complete blood counts every 2 weeks for the first 3 months and then monthly or as clinically indicated. If ANC less than 1 × 10^9/L or platelets less than 50 × 10^9/L, interrupt ICLUSIG until ANC at least 1.5 × 10^9/L and platelets at least 75 × 10^9/L, then resume at same or reduced dose [see Dosage and Administration (2.2)].

5.14 Tumor Lysis Syndrome

In PhALLCON, serious tumor lysis syndrome (TLS) developed in 0.6% of 163 patients. Hyperuricemia occurred in 10% of patients.

In OPTIC, of the 94 patients who received a starting dose of 45 mg, serious TLS developed in 1.1% of patients. Hyperuricemia occurred in 2.1% of patients.

In PACE, serious TLS developed in 0.4% of 449 patients. One case occurred in a patient with advanced AP-CML and 1 case occurred in a patient with BP-CML. Hyperuricemia occurred in 7% of patients.

Ensure adequate hydration and treat high uric acid levels prior to initiating ICLUSIG.

5.15 Reversible Posterior Leukoencephalopathy Syndrome

Reversible posterior leukoencephalopathy syndrome (RPLS; also known as Posterior Reversible Encephalopathy Syndrome) has been reported in patients who received ICLUSIG. Patients can present with hypertension, seizure, headache, decreased alertness, altered mental functioning, vision loss, and other visual and neurological disturbances. Magnetic resonance imaging (MRI) is necessary to confirm the diagnosis. Interrupt ICLUSIG until resolution. The safety of resumption of ICLUSIG in patients upon resolution of RPLS is unknown.

5.16 Impaired Wound Healing and Gastrointestinal Perforation

Impaired wound healing occurred in patients receiving ICLUSIG [see Adverse Reactions (6.2)]. Withhold ICLUSIG for at least 1 week prior to elective surgery. Do not administer for at least 2 weeks following major surgery and until adequate wound healing. The safety of resumption of ICLUSIG after resolution of wound healing complications has not been established.

Gastrointestinal perforation or fistula occurred in patients receiving ICLUSIG [see Adverse Reactions (6.2)]. Permanently discontinue in patients with gastrointestinal perforation.

5.17 Embryo-Fetal Toxicity

Based on its mechanism of action and findings from animal studies, ICLUSIG can cause fetal harm when administered to a pregnant woman. In animal reproduction studies, oral administration of ponatinib to pregnant rats during organogenesis caused adverse developmental effects at exposures lower than human exposures at the maximum recommended human dose of 45 mg/day. Advise pregnant women of the potential risk to the fetus. Advise females of reproductive potential to use effective contraception during treatment with ICLUSIG and for 3 weeks after the last dose [see Use in Specific Populations (8.1, 8.3)].

6 ADVERSE REACTIONS

The following clinically significant adverse reactions are described elsewhere in the labeling:

- Arterial Occlusive Events [see Warnings and Precautions (5.1)]
- Venous Thromboembolic Events [see Warnings and Precautions (5.2)]
- Heart Failure [see Warnings and Precautions (5.3)]
- Hepatotoxicity [see Warnings and Precautions (5.4)]
- Hypertension [see Warnings and Precautions (5.5)]
- Pancreatitis [see Warnings and Precautions (5.6)]
- Neuropathy [see Warnings and Precautions (5.8)]
- Ocular Toxicity [see Warnings and Precautions (5.9)]
- Hemorrhage [see Warnings and Precautions (5.10)]
- Fluid Retention [see Warnings and Precautions (5.11)]
- Cardiac Arrhythmias [see Warnings and Precautions (5.12)]
- Myelosuppression [see Warnings and Precautions (5.13)]
- Tumor Lysis Syndrome [see Warnings and Precautions (5.14)]
- Reversible Posterior Leukoencephalopathy Syndrome [see Warnings and Precautions (5.15)]
- Impaired Wound Healing and Gastrointestinal Perforation [see Warnings and Precautions (5.16)]

6.1 Clinical Trials Experience

Because clinical trials are conducted under widely varying conditions, adverse reaction rates observed in the clinical trials of a drug cannot be directly compared with rates in the clinical trials of another drug and may not reflect the rates observed in clinical practice.

The most common adverse reactions identified in the Highlights of the Prescribing Information are based on two safety populations. The first is from a pooled safety population of 543 patients with CML or resistant or intolerant Ph+ ALL (OPTIC and PACE studies) who received ICLUSIG as a single agent at a starting dose of 45 mg orally once daily. In this pooled safety population, the most common (>20%) adverse reactions were rash and related conditions, arthralgia, abdominal pain, fatigue, headache, constipation, hypertension, dry skin, hepatotoxicity, fluid retention and edema, pyrexia, pancreatitis/lipase elevation, nausea, hemorrhage, anemia, AOEs and cardiac arrhythmias. The most common Grade 3 or 4 laboratory abnormalities (>20%) were platelet count decreased, neutrophil cell count decreased, and white blood cell decreased.

The second safety population is from 163 patients with newly diagnosed Ph+ ALL (PhALLCON study) who received ICLUSIG in combination with chemotherapy at a starting dose of 30 mg orally once daily. The most common adverse reactions (>20%) included hepatotoxicity, arthralgia, rash and related conditions, headache, pyrexia, abdominal pain, constipation, fatigue, nausea, oral mucositis, hypertension, pancreatitis/lipase elevation, neuropathy peripheral, hemorrhage, febrile neutropenia, fluid retention and edema, vomiting, paresthesia, and cardiac arrhythmias. The most common Grade 3 or 4 laboratory abnormalities (>20%) included decreased white blood cell count, decreased neutrophil cell count, decreased platelet count, decreased lymphocyte cell count, decreased hemoglobin, increased lipase, and increased ALT.

Newly Diagnosed Ph+ ALL

The safety of ICLUSIG was evaluated in PhALLCON, a randomized, active-controlled, multicenter trial conducted in patients with newly diagnosed Ph+ ALL [see Clinical Studies (14)]. Patients received ICLUSIG (n=163) or imatinib 600 mg (n=81) in combination with reduced-intensity chemotherapy followed by continued treatment with ICLUSIG or imatinib as a single agent (imatinib in combination with chemotherapy is not an approved regimen in adult patients). In the ICLUSIG arm, patients received a starting dosage of ICLUSIG 30 mg orally once daily in combination with chemotherapy, with a reduction to 15 mg orally once daily upon achievement of MRD-negative CR at the end of induction. The median duration of exposure was 9.0 months (range: <1 month to 4.2 years) in the ICLUSIG arm and 5.2 months (range: <1 month to 4.4 years) in the imatinib arm.

Patients with uncontrolled hypertension, hypertriglyceridemia, or diabetes and patients with clinically significant, uncontrolled, or active cardiovascular disease, including any history of myocardial infarction, peripheral vascular infarction, revascularization procedure, venous thromboembolism, clinically significant atrial/ventricular tachyarrhythmias, history of myocardial infarction, unstable angina, or congestive heart failure within the 6 months prior to the first dose of ICLUSIG, were excluded.

Serious adverse reactions occurred in 63% of patients receiving ICLUSIG in combination with chemotherapy. Serious adverse reactions in >2% of patients included febrile neutropenia (18%), pyrexia (6%), thrombocytopenia (4.3%), sepsis (3.7%), septic shock (3.7%), anemia (2.5%), hemorrhage (2.5%), neutropenia (2.5%), pancreatitis (2.5%), peripheral neuropathy (2.5%), pneumonia (2.5%) and acute kidney injury (2.5%). Fatal adverse reactions occurred in 6% of patients who received ICLUSIG in combination with chemotherapy, including sepsis (3.7%), sudden death, pneumonitis and respiratory failure (0.6%, each).

Permanent discontinuation of ICLUSIG due to adverse reactions occurred in 13% of patients. Adverse reactions resulting in permanent discontinuation of ICLUSIG in >2% of patients included arterial occlusive events and sepsis.

Dosage modifications (dose interruption or reduction) of ICLUSIG due to adverse reactions occurred in 71% of patients. Adverse reactions leading to dose interruption or reduction of ICLUSIG in >5% of patients included increased ALT, neutropenia, increased lipase, thrombocytopenia, increased AST, febrile neutropenia, and abdominal pain.

Table 4 summarizes the adverse reactions in patients receiving ICLUSIG or imatinib in combination with chemotherapy in PhALLCON.

Table 4: Adverse Reactions (>10%) in Patients with Newly Diagnosed Ph+ ALL in PhALLCON
Adverse Reaction | ICLUSIG 30 mg → 15 mg with Chemotherapy (n = 163) |  | Imatinib 600 mg with Chemotherapy (n = 81)
Adverse Reaction | All Grades (%) | Grade 3 or 4 (%) | All Grades (%) | Grade 3 or 4 (%)
Hepatobiliary Disorders
Hepatotoxicity | 66 | 30 | 57 | 14
Musculoskeletal and Connective Tissue Disorders
Arthralgia [Includes arthralgia, arthritis, back pain, flank pain, intervertebral disc degeneration, joint swelling, osteoarthritis, neck pain, pain, pain in extremity, pain of skin, sciatica, spinal pain, tendonitis, and tenosynovitis.] | 47 | 4.3 | 35 | 1.2
Myalgia | 13 | 1.2 | 10 | 1.2
Nervous System Disorders
Headache | 45 | 1.8 | 43 | 1.2
Neuropathy peripheral | 33 | 1.2 | 24 | 1.2
Paresthesia | 22 | 0 | 10 | 0
Peripheral sensory neuropathy | 12 | 0 | 12 | 0
Skin and Subcutaneous Tissue Disorders
Rash and related conditions | 47 | 1.2 | 33 | 1.2
Gastrointestinal Disorders
Abdominal pain [Includes abdominal discomfort, abdominal distension, abdominal pain, abdominal pain lower, abdominal pain upper, chronic gastritis, colitis, enteritis, enterocolitis, gastric ulcer, gastritis, gastroenteritis, gastrointestinal pain, gastroesophageal reflux disease, and helicobacter gastritis.] | 43 | 4.9 | 28 | 0
Constipation | 41 | 0.6 | 21 | 1.2
Nausea | 37 | 3.1 | 52 | 7
Oral mucositis | 35 | 4.9 | 30 | 10
Pancreatitis/lipase elevation | 34 | 15 | 37 | 20
Vomiting | 24 | 1.2 | 40 | 2.5
Diarrhea | 20 | 0 | 35 | 2.5
General Disorders
Pyrexia | 44 | 4.3 | 26 | 2.5
Fatigue or asthenia | 40 | 2.5 | 38 | 3.7
Fluid retention and edema | 24 | 0.6 | 48 | 3.7
Vascular Disorders
Hypertension | 34 | 14 | 15 | 7
Hemorrhage | 31 | 1.8 | 30 | 7
Venous thromboembolic events | 12 | 3.1 | 10 | 2.5
Blood and Lymphatic System Disorders
Febrile neutropenia | 28 | 25 | 22 | 20
Metabolism and Nutrition Disorders
Impaired glucose tolerance | 20 | 4.9 | 20 | 9
Hyperlipidemia | 16 | 1.2 | 15 | 1.2
Decreased appetite | 10 | 0 | 19 | 3.7
Cardiac Disorders
Cardiac arrhythmias | 22 | 2.5 | 17 | 6
Infections
Sepsis [Includes abdominal sepsis, bacteremia, bacterial sepsis, device-related sepsis, escherichia bacteremia, fungemia, klebsiella bacteremia, klebsiella sepsis, neutropenic sepsis, pseudomonal sepsis, sepsis, septic shock, staphylococcal bacteremia, staphylococcal sepsis, streptococcal bacteremia, and urosepsis.] | 17 | 12 | 15 | 11
Pneumonia | 11 | 7 | 11 | 6
Respiratory, Thoracic, and Mediastinal Disorders
Cough | 17 | 0 | 6 | 0
Dyspnea | 13 | 1.2 | 4.9 | 2.5
Graded using CTCAE v5.0

Clinically relevant adverse reactions in ≤10% of patients receiving ICLUSIG with chemotherapy: urinary tract infection (10%), arterial occlusive events (6%), cardiac failure (6%), and acute kidney injury (4.3%).

Table 5 summarizes the laboratory abnormalities in PhALLCON for patients who received ICLUSIG or imatinib in combination with chemotherapy.

Table 5: Select Laboratory Abnormalities (≥20%) that Worsened from Baseline in Patients with Newly Diagnosed Ph+ ALL in PhALLCON
Laboratory Abnormality | ICLUSIG 30 mg → 15 mg with Chemotherapy (n = 163) |  | Imatinib 600 mg with Chemotherapy (n = 81)
Laboratory Abnormality | All Grades (%) | Grade 3 or 4 (%) | All Grades (%) | Grade 3 or 4 (%)
Hematologic Laboratory Tests
White blood cell decreased | 79 | 71 | 78 | 70
Lymphocyte cell count decreased | 77 | 61 | 94 | 89
Neutrophil cell count decreased | 66 | 63 | 57 | 53
Platelet count decreased | 65 | 62 | 64 | 53
Hemoglobin decreased | 53 | 38 | 59 | 49
Liver Function Tests
ALT increased | 69 | 21 | 62 | 7
AST increased | 53 | 7 | 48 | 6
Alkaline phosphatase increased | 44 | 1.2 | 24 | 0
Total bilirubin increased | 25 | 0.6 | 24 | 0
Direct bilirubin increased | 24 | 4.3 | 24 | 1.2
Pancreatic Enzymes
Lipase increased | 60 | 24 | 78 | 38
Amylase increased | 25 | 6 | 35 | 7
Chemistry
Calcium decreased | 67 | 3.1 | 69 | 4.9
Phosphate decreased | 58 | 16 | 85 | 36
Potassium decreased | 44 | 10 | 74 | 25
Albumin decreased | 42 | 1.8 | 56 | 0
Glucose increased | 34 | 2.5 | 38 | 2.5
Creatinine increased | 34 | 3.7 | 48 | 4.9
Sodium decreased | 32 | 3.1 | 35 | 3.7
Potassium increased | 31 | 3.7 | 12 | 0
Magnesium decreased | 15 | 0.6 | 31 | 2.5
ALT = alanine aminotransferase, AST = aspartate aminotransferase
Graded using CTCAE v5.0

Previously Treated CP-CML

The safety of ICLUSIG was evaluated in OPTIC [see Clinical Studies (14)]. Patients received one of three starting doses of ICLUSIG: 45 mg orally once daily (n=94), 30 mg orally once daily (n=94), or 15 mg orally once daily (n=94). Patients with uncontrolled hypertension or diabetes and patients with clinically significant, uncontrolled, or active cardiovascular disease, including any history of myocardial infarction, peripheral vascular infarction, revascularization procedure, congestive heart failure, venous thromboembolism, or clinically significant atrial/ventricular arrhythmias, were excluded. Only the safety information for the recommended starting dosage (45 mg) is described below. Patients who received a starting dose of ICLUSIG 45 mg orally once daily had a mandatory dose reduction to 15 mg once daily upon achievement of ≤1% BCR::ABL1IS. Of these patients, 76% were exposed for 1 year or longer, 59% were exposed for two years or longer and 43% were exposed to five years or longer. The median time to the response-based dose reduction to 15 mg was 6.4 months (range: 3.1 months to 1.8 years).

Serious adverse reactions occurred in 40% of patients who received ICLUSIG at a starting dose of 45 mg. Serious adverse reactions in >2% of patients included AOEs (13%; of which 2.1% were sudden death), cardiac arrhythmias (9%; of which 2.1% were atrial fibrillation), thrombocytopenia (5%), pyrexia (4.3%), anemia (3.2%), abdominal pain (3.2%), pancreatitis/lipase elevation (2.1%), neutropenia (2.1%), hypertension (2.1%) and hepatotoxicity (2.1%). Fatal adverse reactions occurred in 4 patients (4.3%), including sudden death (2.1%), myocardial infarction (1.1%) and myocardial ischemia (1.1%).

Permanent discontinuation of ICLUSIG due to an adverse reaction occurred in 24% of patients who received ICLUSIG at a starting dose of 45 mg. Adverse reactions which resulted in permanent discontinuation in >2% of patients included AOEs, thrombocytopenia, hypertension, and sudden death.

Dose modifications (dose interruption or reductions) of ICLUSIG due to an adverse reaction occurred in 81% of patients who received ICLUSIG at a starting dose of 45 mg. Adverse reactions which required dose interruptions or reductions in >5% of patients included thrombocytopenia, pancreatitis/lipase elevation, neutropenia, hepatotoxicity, rash and related conditions, anemia, cardiac arrhythmias, AOEs, and cardiac failure.

The most common (>20%) adverse reactions were rash and related conditions, hypertension, hepatoxicity, hyperlipidemia, arthralgia, pancreatitis/lipase elevation, abdominal pain and cardiac arrhythmias. The most common (>20%) Grade 3 or 4 laboratory abnormalities were platelet count decreased and neutrophil cell count decreased.

Table 6 summarizes the adverse reactions in OPTIC for patients who received ICLUSIG at a starting dose of 45 mg.

Table 6: Adverse Reactions (≥10%) in Patients with CP-CML Who Received ICLUSIG at Starting Dose of 45 mg Followed by Reduction to 15 mg After Achievement of ≤1% BCR::ABL1IS in OPTIC
Adverse Reaction | ICLUSIG 45 mg → 15 mg (N = 94)
Adverse Reaction | All Grades (%) | Grade 3 or 4 (%)
Skin and Subcutaneous Tissue Disorders
Rash and related conditions | 47 | 3.2
Dry skin | 12 | 0
Vascular Disorders
Hypertension | 37 | 14
Arterial occlusive events | 18 | 7
Hemorrhage | 13 | 2.1
Hepatobiliary Disorders
Hepatotoxicity | 34 | 7
Musculoskeletal and Connective Tissue Disorders
Arthralgia [Arthralgia includes arthralgia, back pain, osteoarthritis, pain, neck pain, pain in extremity, spinal pain, tendonitis, bone pain, musculoskeletal pain, chondrocalcinosis, enthesopathy, pain in jaw] | 33 | 0
Metabolism and Nutrition Disorders
Hyperlipidemia [Hyperlipidemia includes blood cholesterol increased, blood triglycerides increased, dyslipidemia, hypercholesterolemia, hyperlipidemia, hypertriglyceridemia, low density lipoprotein increased] | 32 | 4.3
Impaired glucose tolerance | 10 | 2.1
Gastrointestinal Disorders
Abdominal pain [Abdominal pain includes abdominal distension, abdominal pain, abdominal pain upper, chronic gastritis, duodenal ulcer, duodenitis, duodenogastric reflux, dyspepsia, gastric ulcer, gastritis, gastroenteritis, gastrointestinal pain, helicobacter gastritis, peptic ulcer] | 31 | 3.2
Pancreatitis/lipase elevation | 29 | 16
Constipation | 15 | 0
Cardiac Disorders
Cardiac arrhythmias | 27 | 5
Cardiac failure | 20 | 2.1
Nervous System Disorders
Headache | 20 | 0
Neuropathy | 13 | 0
General Disorders and Administration Site Conditions
Pyrexia | 18 | 1.1
Fatigue or asthenia | 18 | 1.1
Infections and Infestations
Upper respiratory tract infection | 11 | 0
Respiratory Thoracic and Mediastinal Disorders
Cough | 10 | 0
Graded using CTCAE v5.0

Clinically relevant adverse reactions in <10% of patients who received ICLUSIG at a starting dose of 45 mg: fluid retention and edema (6%), and hypothyroidism (5%).

Table 7 summarizes the laboratory abnormalities in OPTIC for patients who received ICLUSIG at a starting dose of 45 mg.

Table 7: Select Laboratory Abnormalities (>20%) that Worsened from Baseline in Patients with CP-CML Who Received ICLUSIG at Starting Dose of 45 mg in OPTIC
Laboratory Abnormality | ICLUSIG 45 mg → 15 mg (N = 94)
Laboratory Abnormality | All Grades (%) | Grade 3 or 4 (%)
Hematologic Laboratory Tests
Platelet count decreased | 66 | 31
Neutrophil cell count decreased | 56 | 22
White blood cell decreased | 54 | 15
Lymphocyte decreased | 45 | 9
Hemoglobin decreased | 38 | 14
Liver Function Tests
ALT increased | 53 | 2.1
AST increased | 39 | 1.1
Alkaline phosphatase increased | 31 | 1.1
Chemistry
Glucose increased | 53 | 3.2
Triglycerides increased | 50 | 6
Phosphate decreased | 34 | 3.2
Bicarbonate decreased | 30 | 0
Calcium decreased | 21 | 3.2
Pancreatic Enzymes
Lipase increased | 40 | 16
ALT = alanine aminotransferase, AST = aspartate aminotransferase
Graded using CTCAE v5.0 (except glucose increased which is graded using CTCAE v4.03)

Previously Treated CML or Ph+ ALL

The safety of ICLUSIG was evaluated in PACE [see Clinical Studies (14)]. Eligible patients had CML or Ph+ ALL whose disease was considered to be resistant or intolerant to prior kinase inhibitor, including those with the BCR::ABL T315I mutation. Patients with uncontrolled hypertriglyceridemia and patients with clinically significant or active cardiovascular disease, including any history of clinically significant atrial/ventricular arrhythmias or history of myocardial infarction, unstable angina, or congestive heart failure within the 3 months prior to the first dose of ICLUSIG, were excluded. Patients received a starting dose of ICLUSIG 45 mg orally once daily (N=449). Dose reductions to 30 mg orally once daily or 15 mg orally once daily were allowed for the management of adverse reactions. After approximately 2 years of follow-up, patients who were still taking a 45 mg orally once daily dose were recommended to undergo a dose reduction in response to the continued occurrence of AOEs and VTEs in the clinical trial [see Warnings and Precautions (5.1)]. At study completion (60 months of follow-up), the median duration of treatment with ICLUSIG was 32 months in patients with CP-CML, 19 months in patients with AP-CML, 2.9 months in patients with BP-CML, and 2.7 months in patients with Ph+ ALL.

Serious adverse reactions occurred in 69% of patients who received ICLUSIG. Serious adverse reactions in >2% of patients included AOEs (20%), pneumonia (10%), cardiac arrhythmias (8%), pancreatitis/lipase elevation (7%), abdominal pain (6%), cardiac failure (6%), hemorrhage (6%), sepsis (5%), VTEs (5%), fluid retention and edema (4.5%), pyrexia (4.5%), secondary malignancies (5%), anemia (3.3%), hypertension (3.1%), thrombocytopenia (3.1%), febrile neutropenia (2.9%), cellulitis (2.7%), and arthralgia (2.2%). Fatal adverse reactions occurred in 9% of patients who received ICLUSIG; the most frequent fatal adverse reactions were AOEs (2%), sepsis (1.6%), and hemorrhage (1.3%).

Permanent discontinuation of ICLUSIG due to an adverse reaction occurred in 21% of CP-CML, 12% of AP-CML, 15% of BP-CML, and 9% of Ph+ ALL patients. The most frequent adverse reactions that led to treatment discontinuation were thrombocytopenia (4.5%) and AOEs (4%).

Dose interruption of ICLUSIG for more than 3 days due to an adverse reaction occurred in 71% of patients and dose reduction of ICLUSIG due to an adverse reaction occurred in 68% of patients. Adverse reactions which required a dosage interruption or dose reduction in >5% of patients included thrombocytopenia (31%), pancreatitis/lipase elevation (17%), abdominal pain (14%), rash and related conditions (14%), neutropenia (14%), hepatotoxicity (12%), AOEs (10%), arthralgia (8%), anemia (7%), ALT increased (6%), and AST increased (5%).

The most common (>20%) non-hematologic adverse reactions were rash and related conditions, arthralgia, abdominal pain, fatigue, constipation, headache, dry skin, fluid retention and edema, hepatotoxicity, hypertension, pyrexia, nausea, hemorrhage, pancreatitis/lipase elevation, AOEs, diarrhea, vomiting, and myalgia.

Table 8 summarizes the adverse reactions in PACE.

Table 8: Adverse Reactions (>10%) in Patients with CML or Ph+ ALL Who Received ICLUSIG in PACE
Adverse Reaction | CP-CML (N = 270) |  | AP-CML (N = 85) |  | BP-CML (N = 62) |  | Ph+ ALL (N = 32)
Adverse Reaction | All Grades (%) | Grade 3 or 4 (%) | All Grades (%) | Grade 3 or 4 (%) | All Grades (%) | Grade 3 or 4 (%) | All Grades (%) | Grade 3 or 4 (%)
Skin and Subcutaneous Tissue Disorders
Rash and related conditions | 75 | 9 | 68 | 12 | 55 | 7 | 50 | 3.1
Dry skin | 42 | 3.3 | 32 | 1.2 | 26 | 1.6 | 25 | 0
Alopecia | 8 | 0 | 11 | 0 | 8 | 0 | 6 | 0
Musculoskeletal and Connective Tissue Disorders
Arthralgia | 61 | 9 | 58 | 6 | 52 | 4.8 | 41 | 0
Myalgia | 24 | 1.1 | 21 | 0 | 18 | 0 | 6 | 0
Muscle spasms | 14 | 0 | 7 | 0 | 4.8 | 0 | 13 | 0
Bone pain | 14 | 0.4 | 13 | 1.2 | 11 | 3 | 9 | 3
Musculoskeletal pain | 11 | 1.5 | 7 | 0 | 8.1 | 0 | 6 | 3
Gastrointestinal Disorders
Abdominal pain | 54 | 11 | 49 | 9 | 45 | 13 | 34 | 6
Constipation | 42 | 2.6 | 29 | 2.4 | 27 | 0 | 53 | 3.1
Pancreatitis/lipase elevation | 32 | 19 | 21 | 15 | 19 | 16 | 9 | 6
Nausea | 29 | 0.7 | 32 | 0 | 34 | 1.6 | 22 | 0
Diarrhea | 20 | 0.7 | 29 | 2.4 | 24 | 3.2 | 13 | 3.1
Vomiting | 19 | 1.5 | 27 | 0 | 27 | 1.6 | 25 | 0
Oral mucositis [Oral mucositis includes aphthous ulcer, gingival pain, lip blister, lip pain, lip swelling, mouth ulceration, oropharyngeal pain, oral mucosal blistering, oral mucosal eruption, oral pain, pharyngeal ulceration, stomatitis, and tongue ulceration] | 16 | 1.1 | 20 | 1.2 | 24 | 0 | 9 | 3.1
General Disorders
Fatigue or asthenia | 44 | 3.7 | 47 | 8 | 36 | 4.8 | 34 | 3.1
Fluid retention and edema | 31 | 3.7 | 37 | 3.5 | 32 | 4.8 | 41 | 6
Pyrexia | 26 | 1.1 | 40 | 7 | 37 | 3.2 | 25 | 0
Chills | 8 | 0 | 12 | 0 | 13 | 1.6 | 9 | 0
Nervous System Disorders
Headache | 43 | 3.3 | 31 | 1.2 | 31 | 3.2 | 25 | 0
Neuropathy | 26 | 3.3 | 18 | 2.4 | 13 | 0 | 13 | 0
Dizziness | 17 | 0.4 | 11 | 0 | 4.8 | 0 | 3.1 | 0
Vascular Disorders
Hypertension [Derived from blood pressure (BP) measurement] | 42 | 30 | 53 | 28 | 48 | 6 | 31 | 25
Arterial occlusive events | 31 | 17 | 22 | 12 | 13 | 10 | 13 | 6
Hemorrhage | 23 | 3 | 38 | 12 | 37 | 8 | 31 | 13
Hepatobiliary Disorders
Hepatotoxicity | 32 | 10 | 39 | 14 | 34 | 19 | 16 | 13
Cardiac Disorders
Cardiac arrhythmias | 19 | 7 | 17 | 4.7 | 24 | 8 | 25 | 6
Cardiac failure | 9 | 5 | 8 | 4.7 | 16 | 10 | 6 | 3.1
Respiratory, Thoracic, and Mediastinal Disorders
Cough [Cough includes cough, productive cough, and upper airway cough syndrome] | 19 | 0 | 24 | 0 | 21 | 0 | 6 | 0
Dyspnea [Dyspnea includes dyspnea and dyspnea exertional] | 19 | 3 | 20 | 3.5 | 23 | 6 | 16 | 0
Infections
Upper respiratory tract infection [Upper respiratory tract infection includes upper respiratory tract infection and viral upper respiratory tract infection] | 14 | 1.1 | 13 | 0 | 13 | 1.6 | 3.1 | 0
Urinary tract infection [Urinary tract infection includes escherichia urinary tract infection, urinary tract infection, and urinary tract infection bacterial] | 12 | 2.2 | 14 | 3.5 | 1.6 | 1.6 | 9 | 0
Nasopharyngitis | 12 | 0 | 18 | 0 | 3.2 | 0 | 3.1 | 0
Pneumonia | 8 | 4.8 | 18 | 11 | 18 | 13 | 22 | 16
Cellulitis | 4.4 | 1.9 | 8 | 3.5 | 13 | 4.8 | 0 | 0
Sepsis [Sepsis includes abdominal sepsis, bacteremia, device-related sepsis, escherichia bacteremia, fungemia, klebsiella bacteremia, klebsiella sepsis, neutropenic sepsis, sepsis, septic shock, staphylococcal bacteremia, staphylococcal sepsis, streptococcal bacteremia, and urosepsis] | 2.6 | 1.9 | 11 | 6 | 18 | 6 | 28 | 25
Metabolism and Nutrition Disorders
Decreased appetite | 13 | 0.4 | 14 | 1.2 | 8 | 0 | 31 | 0
Hyperlipidemia | 13 | 0.7 | 7 | 0 | 3.2 | 0 | 3.1 | 0
Investigations
Weight decreased | 10 | 0.4 | 9 | 0 | 4.8 | 0 | 13 | 0
Psychiatric Disorders
Insomnia | 11 | 0 | 13 | 0 | 11 | 0 | 13 | 0
Anxiety | 4.8 | 0 | 18 | 0 | 8 | 0 | 6 | 0
Blood and Lymphatic System Disorders
Febrile neutropenia | 1.1 | 1.1 | 4.7 | 4.7 | 13 | 13 | 25 | 25
Graded using CTCAE v4.03.

Clinically relevant adverse reactions occurring in ≤10% of patients: impaired glucose tolerance (9%) [Grouped terms: secondary malignancies includes basal cell carcinoma, squamous cell carcinoma of the skin, melanoma, chronic myelomonocytic leukemia, colon cancer, epithelioid mesothelioma, large cell lung cancer recurrent, lung neoplasm, malignant ascites, myelodysplastic syndrome, neuroendocrine carcinoma metastatic, non-Hodgkin lymphoma, pancreatic cancer, thyroid neoplasm, vulval cancer; venous thromboembolic events includes deep vein thrombosis, pulmonary embolism, retinal vein occlusion, retinal vein thrombosis, superficial thrombophlebitis, venous embolism, veno-occlusive liver disease, portal vein thrombosis; impaired glucose tolerance includes blood glucose increased, diabetes mellitus, glucose tolerance impaired, glycosylated hemoglobin increased, hyperglycemia, insulin resistance, and type 2 diabetes mellitus] , venous thromboembolic events (6%), secondary malignancies (6%), and hypothyroidism (3%).

Tables 9 and 10 summarize the Grade 3 or 4 hematologic laboratory abnormalities or all grades non-hematologic abnormalities in PACE.

Table 9: Select Grade 3 or 4 [Graded using CTCAE v4.03] Hematologic Laboratory Abnormalities in Patients Who Received ICLUSIG in PACE
Laboratory Abnormality | CP-CML (N = 270) (%) | AP-CML (N = 85) (%) | BP-CML (N = 62) (%) | Ph+ ALL (N = 32) (%)
Hematology
Platelet count decreased | 35 | 49 | 45 | 47
Neutrophil cell count decreased | 23 | 52 | 48 | 59
White blood cell decreased | 12 | 37 | 48 | 63
Lymphocyte decreased | 10 | 25 | 32 | 19
Hemoglobin decreased | 8 | 31 | 52 | 34

Table 10: Select Non-Hematologic Laboratory Abnormalities (≥20%) in Patients Who Received ICLUSIG in PACE
Laboratory Abnormality | Pooled Safety Population (N = 449)
Laboratory Abnormality | All Grades [Graded using CTCAE v4.03] (%) | Grade 3 or 4 (%)
Chemistry
Glucose increased | 54 | 7
Phosphate decreased | 34 | 10
Calcium decreased | 30 | 0.9
Sodium decreased | 27 | 4.9
Creatinine increased | 21 | 0.2
Potassium increased | 20 | 2.2
Bicarbonate decreased | 20 | 0.2
Liver Function Tests
ALT increased | 41 | 6
Alkaline phosphatase increased | 40 | 2
AST increased | 35 | 3.6
Albumin decreased | 28 | 0.2
Bilirubin increased | 13 | 0.9
Pancreatic Enzymes
Lipase increased | 40 | 14
Amylase increased | 18 | 3.6
ALT = alanine aminotransferase, AST = aspartate aminotransferase

6.2 Postmarketing Experience

The following adverse reactions have been identified during post-approval use of ICLUSIG. Because these reactions are reported voluntarily from a population of uncertain size, it is not always possible to reliably estimate their frequency or establish a causal relationship to drug exposure:

Blood and Lymphatic System Disorders: Thrombotic microangiopathy

Endocrine Disorders: Hyperthyroidism

Gastrointestinal Disorders: Gastrointestinal perforation, fistula

Metabolism and Nutrition Disorders: Dehydration

Nervous System Disorders: Reversible posterior leukoencephalopathy syndrome (RPLS)

Skin and Subcutaneous Tissue Disorders: Severe cutaneous reaction (e.g., Erythema multiforme, Stevens-Johnson syndrome), impaired wound healing, panniculitis (including erythema nodosum)

Vascular Disorders: Arterial (including aortic) aneurysms, dissections, and rupture

7 DRUG INTERACTIONS

7.1 Effects of Other Drugs on ICLUSIG

Strong CYP3A Inhibitors

Coadministration of ICLUSIG with a strong CYP3A inhibitor increases ponatinib plasma concentrations [see Clinical Pharmacology (12.3)], which may increase the risk of ICLUSIG adverse reactions. Avoid coadministration of ICLUSIG with strong CYP3A inhibitors. If coadministration of ICLUSIG with strong CYP3A inhibitors cannot be avoided, reduce the ICLUSIG dosage [see Dosage and Administration (2.3)].

Strong CYP3A Inducers

Coadministration of ICLUSIG with a strong CYP3A inducer decreases ponatinib plasma concentrations [see Clinical Pharmacology (12.3)]. Avoid coadministration of ICLUSIG with strong CYP3A inducers unless the benefit outweighs the risk of decreased ponatinib exposure. Monitor patients for reduced efficacy. Selection of concomitant medication with no or minimal CYP3A induction potential is recommended.

8 USE IN SPECIFIC POPULATIONS

8.1 Pregnancy

Risk Summary

Based on findings in animals and its mechanism of action [see Clinical Pharmacology (12.1)], ICLUSIG can cause fetal harm when administered to a pregnant woman. There are no available data on ICLUSIG use in pregnant women. In animal reproduction studies, oral administration of ponatinib to pregnant rats during organogenesis caused adverse developmental effects at doses lower than human exposures at the maximum recommended human dose of 45 mg/day (see Data). Advise pregnant women of the potential risk to a fetus.

In the U.S. general population, the estimated background risk of major birth defects and miscarriage in clinically recognized pregnancies is 2% to 4% and 15% to 20%, respectively.

Data

Animal Data

Ponatinib was studied for effects on embryo-fetal development in pregnant rats given oral doses of 0.3 mg/kg/day, 1 mg/kg/day, and 3 mg/kg/day during organogenesis (25 rats per group). At the maternally toxic dose of 3 mg/kg/day (equivalent to the AUC in patients receiving the maximum recommended dose of 45 mg/day), ponatinib caused embryo-fetal toxicity as shown by increased resorptions, reduced body weight, external alterations, multiple soft tissue and skeletal alterations, and reduced ossification. Embryo-fetal toxicities also were observed at 1 mg/kg/day (approximately 24% the AUC in patients receiving the maximum recommended dose of 45 mg/day) and involved multiple fetal soft tissue and skeletal alterations, including reduced ossification.

8.2 Lactation

Risk Summary

There are no data on the presence of ponatinib in human milk, the effects on the breastfed child, or on milk production. Because of the potential for serious adverse reactions in the breastfed child, advise women not to breastfeed during treatment with ICLUSIG and for 1 week after the last dose.

8.3 Females and Males of Reproductive Potential

ICLUSIG can cause fetal harm when administered to pregnant women [see Use in Specific Populations (8.1)].

Pregnancy Testing

Verify the pregnancy status of females of reproductive potential prior to initiating ICLUSIG.

Contraception

Females

Advise females of reproductive potential to use effective contraception during treatment with ICLUSIG and for 3 weeks after the last dose.

Infertility

Females

Based on animal data, ponatinib may impair fertility in females of reproductive potential [see Nonclinical Toxicology (13.1)]. It is not known whether these effects on fertility are reversible.

8.4 Pediatric Use

Safety and effectiveness of ICLUSIG have not been established in pediatric patients.

Juvenile Animal Toxicity Data

A juvenile toxicity study in 15 day old rats was conducted with daily oral gavage administration of ponatinib at 0.75 mg/kg/day, 1.5 mg/kg/day, or 3 mg/kg/day for 21 days. There were no adverse effects of ponatinib on juvenile rat developmental parameters (vaginal opening, preputial separation or bone measurements) observed in this study. Once daily oral administration of 3 mg/kg/day ponatinib to juvenile rats beginning on Day 15 postpartum (pp) resulted in mortality related to inflammatory effects after 6 to 7 days following initiation of treatment. The dose of 3 mg/kg/day is approximately 0.32 times the maximum recommended human dose of 45 mg/day on a mg/m^2 basis for a child.

8.5 Geriatric Use

Of the 163 patients with Ph+ALL who received ICLUSIG in PhALLCON, 21% were 65 years and older and 7% were 75 years and older. Overall, no differences in efficacy of ICLUSIG were observed between patients 65 years of age or older compared to younger patients. AOEs occurred in 21% (7/34) of patients 65 years and older and 2.3% (3/129) of patients less than 65 years of age.

Of the 94 patients with CP-CML who received ICLUSIG at a starting dose of 45 mg in OPTIC, 17% were 65 years and older and 2.1% were 75 years and older. Patients aged 65 years and older had a lower ≤1% BCR::ABL1IS rate at 12 months (27%) than patients less than 65 years of age (47%). By 60 months, patients aged 65 years and older had a ≤1% BCR::ABL1IS rate of 40% and patients less than 65 years of age had a rate of 64%. AOEs occurred in 38% (6/16) of patients 65 years and older and 14% (11/78) of patients less than 65 years of age [see Warnings and Precautions (5.1)].

Of the 449 patients who received ICLUSIG in PACE, 35% were 65 years and older and 8% were 75 years and older. In patients with CP-CML, patients aged 65 years and older had a lower major cytogenetic response rate (40%) as compared with patients less than 65 years of age (65%). In patients with AP-CML, BP-CML, and Ph+ ALL, patients aged 65 years and older had a similar hematologic response rate (45%) as compared with patients less than 65 years of age (44%). AOEs occurred in 35% (54/155) of patients 65 years and older and in 21% (61/294) of patients less than 65 years of age [see Warnings and Precautions (5.1)].

Patients aged 65 years or older are more likely to experience adverse reactions including vascular occlusion, decreased platelet count, peripheral edema, increased lipase, dyspnea, asthenia, muscle spasms, and decreased appetite. In general, dose selection for an elderly patient should be cautious, reflecting the greater frequency of decreased hepatic, renal, or cardiac function, and of concomitant disease or other drug therapy.

8.6 Hepatic Impairment

Patients with hepatic impairment are more likely to experience adverse reactions compared to patients with normal hepatic function. For patients with CP-CML, AP-CML, BP-CML, and Ph+ ALL receiving monotherapy, reduce the starting dose of ICLUSIG for patients with pre-existing hepatic impairment (Child-Pugh A, B, or C). For patients with newly diagnosed Ph+ ALL, dosage adjustment is not recommended when administering ICLUSIG to patients with mild hepatic impairment (Child-Pugh A). Clinical data in patients with newly diagnosed Ph+ ALL with pre-existing moderate or severe hepatic impairment (Child-Pugh B or C) is not available and patients should be closely monitored for potential increased incidence of adverse reactions. Modify the ICLUSIG dosage in the event of adverse reactions [see Dosage and Administration (2.2, 2.4), Clinical Pharmacology (12.3)]. The safety of multiple doses, or doses higher than 30 mg, has not been studied in patients with hepatic impairment.

10 OVERDOSAGE

Overdoses with ICLUSIG were reported in clinical trials. One patient was estimated to have been administered 540 mg via nasogastric tube. Two hours after the overdosage, the patient had an uncorrected QT interval of 520 ms. Subsequent ECGs showed normal sinus rhythm with uncorrected QT intervals of 480 ms and 400 ms. The patient died 9 days after the overdosage from pneumonia and sepsis. Another patient self-administered 165 mg on Cycle 1 Day 2. The patient experienced fatigue and non-cardiac chest pain on Day 3. Multiple doses of 90 mg per day for 12 days in a patient resulted in pneumonia, systemic inflammatory response, atrial fibrillation, and a moderate pericardial effusion.

In the event of an overdosage, stop ICLUSIG, observe the patient and provide supportive treatment as appropriate.

11 DESCRIPTION

Ponatinib is a kinase inhibitor. The chemical name for ponatinib hydrochloride is 3-(imidazo[1,2-b]pyridazin-3-ylethynyl)-4-methyl-N-{4-[(4-methylpiperazin-1-yl)methyl]-3-(trifluoromethyl)phenyl}benzamide hydrochloride. The molecular formula is C29H28ClF3N6O which corresponds to a formula weight of 569.02 g/mol. Its structure is shown below:

Ponatinib HCl is an off-white to yellow powder with pKa of 2.77 and 7.8. The solubility of ponatinib in pH 1.7, 2.7, and 7.5 buffers is 7790 mcg/mL, 3.44 mcg/mL, and 0.16 mcg/mL, respectively, indicating a decrease in solubility with increasing pH. Each tablet for oral administration contains 10 mg, 15 mg, 30 mg or 45 mg of ponatinib equivalent to 10.68 mg, 16.03 mg, 32.05 mg, and 48.08 mg of ponatinib hydrochloride with the following inactive ingredients: lactose monohydrate, microcrystalline cellulose, sodium starch glycolate (type B), colloidal silicon dioxide, magnesium stearate and a tablet coating. The tablet coating consists of talc, polyethylene glycol, polyvinyl alcohol, and titanium dioxide.

12 CLINICAL PHARMACOLOGY

12.1 Mechanism of Action

Ponatinib is a kinase inhibitor. Ponatinib inhibited the in vitro tyrosine kinase activity of ABL and T315I mutant ABL with IC50 concentrations of 0.4 nM and 2.0 nM, respectively. Ponatinib inhibited the in vitro activity of additional kinases with IC50 concentrations between 0.1 nM and 20 nM, including members of the VEGFR, PDGFR, FGFR, EPH receptors and SRC families of kinases, and KIT, RET, TIE2, and FLT3. Ponatinib inhibited the in vitro viability of cells expressing native or mutant BCR::ABL, including T315I. In mice, treatment with ponatinib reduced the size of tumors expressing native or T315I mutant BCR::ABL when compared to controls.

12.2 Pharmacodynamics

In PACE, the dose intensity-safety relationship indicated that there are significant increases in Grade ≥3 adverse reactions (hypertension, thrombocytopenia, pancreatitis, neutropenia, rash, ALT increase, AST increase, lipase increase, myelosuppression) over the dose range of 15 mg to 45 mg. In addition to dose, increased age and history of ischemia, hypertension, diabetes, or hypercholesterolemia were also contributory factors to a higher incidence of AOEs.

In OPTIC, an exposure-response relationship between ponatinib exposure and molecular response rate at 12 months was observed. A relationship between higher ponatinib exposures and higher incidence of adverse reactions, including thrombocytopenia (Grade ≥3) and AOEs, was observed.

In vitro, there was no significant inhibition of platelet aggregation with ponatinib at concentrations seen clinically and up to 0.7 mcg/mL (1.23 μM).

Cardiac Electrophysiology

The QT interval prolongation potential of ICLUSIG was assessed in 39 patients with cancer who received ICLUSIG 30 mg, 45 mg, or 60 mg (0.67 to 1.33 times the approved maximum recommended starting dose) orally once daily. No large mean increase (i.e., >20 msec) in QTc interval was detected.

12.3 Pharmacokinetics

Ponatinib administered to patients with cancer exhibited approximately dose proportional increases in both steady-state Cmax and AUC over the dose range of 2 mg to 60 mg (0.04 to 1.33 times the approved maximum recommended starting dose). The mean (CV%) Cmax and AUC(0-24) of ICLUSIG 45 mg orally once daily at presumed steady-state in patients with advanced hematologic malignancies were 73 ng/mL (74%) and 1253 ng∙hr/mL (73%), respectively. The mean (CV%) Cmax and AUC(0-24) of ICLUSIG 30 mg orally once daily at presumed steady-state in patients with advanced hematologic malignancies were 65 ng/mL (28%) and 1080 ng∙hr/mL (29%), respectively. Exposure increased by approximately 90% (median) [range: 20% to 440%] between the first dose and presumed steady-state.

Absorption

The absolute bioavailability of ponatinib is unknown. Peak concentrations of ponatinib are observed within 6 hours after ICLUSIG oral administration.

Effect of Food
Following ingestion of either a high-fat (approximately 900 to 1000 calories with approximately 150, 250, and 500 to 600 calories derived from protein, carbohydrate, and fat, respectively) or low-fat meal (approximately 547 calories with approximately 56, 428 and 63 calories derived from protein, carbohydrate, and fat, respectively) by 22 healthy volunteers, plasma ponatinib exposures (AUC and Cmax) were not different when compared to fasting conditions.

Distribution

Ponatinib is greater than 99% bound to plasma proteins in vitro. There was no plasma protein binding displacement of ponatinib (145 nM) in vitro by other highly protein bound medications (ibuprofen, nifedipine, propranolol, salicylic acid, and warfarin).

The mean (CV%) apparent steady-state volume of distribution is 1,223 liters (102%) following oral administration of ICLUSIG 45 mg orally once daily for 28 days in patients with cancer.

Elimination

The mean (range) terminal elimination half-life of ponatinib was approximately 24 (12 to 66) hours following ICLUSIG 45 mg orally once daily for 28 days in patients with cancer.

Metabolism

At least 64% of a dose undergoes Phase I and Phase II metabolism. CYP3A4 and to a lesser extent CYP2C8, CYP2D6 and CYP3A5 are involved in the Phase I metabolism of ponatinib in vitro. Ponatinib is also metabolized by esterases and/or amidases.

Excretion

Following a single oral dose of radiolabeled ponatinib, approximately 87% of the radioactive dose was recovered in the feces and approximately 5% in the urine.

Specific Populations

No clinically significant differences in the pharmacokinetics of ponatinib were observed based on age (19 to 85 years), body weight (41 to 152 kg), and mild to moderate renal impairment (creatinine clearance 30 to 89 mL/min, estimated by the Cockcroft-Gault equation).

Patients with Renal Impairment

ICLUSIG has not been studied in patients with severe renal impairment. Although renal excretion is not a major route of ponatinib elimination, the potential for severe renal impairment to affect hepatic elimination has not been determined.

Patients with Hepatic Impairment

A single 30 mg oral dose of ICLUSIG was administered to subjects with normal hepatic function and to subjects with mild (Child-Pugh A), moderate (Child-Pugh B), and severe (Child-Pugh C) hepatic impairment. Compared to subjects with normal hepatic function, there was no trend of increased ponatinib exposure in subjects with hepatic impairment. There was an increased incidence of adverse reactions (e.g., gastrointestinal disorders, including a case of severe pancreatitis) in subjects with hepatic impairment compared to subjects with normal hepatic function.

Drug Interaction Studies

Clinical Studies

Strong CYP3A Inhibitors: Coadministration of ponatinib with multiple doses of ketoconazole (strong CYP3A inhibitor) increased the ponatinib AUC0-INF by 78% and Cmax by 47%.

Strong CYP3A Inducers: Coadministration of ponatinib with multiple doses of rifampin (strong CYP3A inducer) decreased the ponatinib AUC0-INF by 62% and Cmax by 42%.

Gastric Acid Reducing Agents: Coadministration of ponatinib with multiple doses of lansoprazole (proton pump inhibitor) decreased the ponatinib AUC0-INF by 6% and Cmax by 25%.

In Vitro Studies

CYP Enzymes: Ponatinib does not inhibit CYP1A2, CYP2B6, CYP2C8, CYP2C9, CYP2C19, CYP3A, or CYP2D6 and does not induce CYP1A2, CYP2B6, or CYP3A.

Transporter Systems: Ponatinib is a weak substrate for both P-glycoprotein (P-gp) and breast cancer resistance protein (BCRP). Ponatinib is not a substrate for organic anion transporting polypeptides (OATP1B1, OATP1B3) and organic cation transporter 1 (OCT1).

Ponatinib inhibits P-gp, BCRP, and bile salt export pump (BSEP). Ponatinib does not inhibit OATP1B1, OATP1B3, OCT1, OCT2, or the organic anion transporters OAT1 and OAT3.

13 NONCLINICAL TOXICOLOGY

13.1 Carcinogenesis, Mutagenesis, Impairment of Fertility

In a 2 year carcinogenicity study, male and female rats were administered daily oral doses of ponatinib of 0.05 mg/kg/day, 0.1 mg/kg/day, 0.2 mg/kg/day and 0.2 mg/kg/day, 0.4 mg/kg/day, and 0.8 mg/kg/day, respectively. Exposures in animals at the highest dose tested were 0.3- to 0.8-fold the human exposure (based on AUC) at doses of 15 mg and 45 mg daily. Ponatinib induced a statistically significant increase in malignant squamous neoplasms of the clitoral gland in females at 0.8 mg/kg/day.

Ponatinib was not mutagenic in a bacterial mutagenesis (Ames) assay, was not clastogenic in a chromosome aberration assay in human lymphocytes, nor was it clastogenic in an in vivo mouse micronucleus assay at oral doses up to 2000 mg/kg.

Ponatinib may impair female fertility. In a fertility study in male and female rats, female fertility parameters were reduced at 1.5 mg/kg/day with exposure equivalent to 0.43 times and 1.23 times of human daily steady-state AUC at the maximum recommended human dose of 45 mg/day (AUC = 1296 h∙ng/mL) and 15 mg/day (451.8 h∙ng/mL), respectively. Evidence of pre- and post-implantation loss of embryos was observed in female rats. Although there were no effects on male fertility parameters in the rat fertility study, repeat dose toxicology studies in monkeys showed degeneration of epithelium of the testes in monkeys at exposures approximately 3.3 times the plasma drug exposure (AUC) in patients receiving the maximum recommended human dose of 45 mg/day.

14 CLINICAL STUDIES

Newly Diagnosed Ph+ ALL

The efficacy of ICLUSIG in combination with chemotherapy was evaluated in PhALLCON (NCT03589326), a randomized, active-controlled, multicenter, open-label trial of 245 patients with newly diagnosed Ph+ ALL. Randomization was stratified by age at the time of induction therapy (18 to <45 years; ≥45 to <60 years; and ≥60 years). Patients were randomized (2:1) to receive either ICLUSIG 30 mg orally once daily (n=164) or imatinib 600 mg orally once daily (n=81) in combination with chemotherapy (imatinib in combination with chemotherapy is an unapproved regimen in adult patients). The ICLUSIG dose was reduced to 15 mg once daily after completion of the induction phase and achievement of MRD-negative complete remission (CR). If a patient lost MRD negativity at any time after dose reduction to 15 mg, re-escalation to 30 mg once daily was allowed. Only patients who achieved CR or CR with incomplete hematologic recovery (CRi) with MRD-negativity at the end of induction could continue study treatment at the investigator’s discretion.

Per protocol, patients were allowed to receive one cycle of optional prephase therapy excluding TKI prior to randomization to manage the acute disease during the screening period.

Patients were randomized to receive either ICLUSIG or imatinib in combination with 20 cycles of chemotherapy, followed by ICLUSIG or imatinib as single-agent therapy (ICLUSIG or imatinib as single-agent after chemotherapy for newly diagnosed Ph+ ALL is not an approved regimen). Each cycle lasted 28 days.

- Induction (Cycles 1 to 3): ICLUSIG 30 mg or imatinib 600 mg once daily in combination with:
  - Vincristine: 1.4 mg/m^2 IV on Days 1 and 14; capped at 2 mg and
  - Dexamethasone: <60 years old – 40 mg orally on Days 1 to 4 and Days 11 to 14; ≥60 years old: 20 mg orally on Days 1 to 4 and Days 11 to 14.

- Consolidation (Cycles 4 to 9, alternating methotrexate and cytarabine): ICLUSIG 30 mg (or decreased to 15 mg if in MRD-negative CR) or imatinib 600 mg once daily in combination with:
  - Methotrexate (Cycles 4, 6, and 8): <60 years old – 1000 mg/m^2 IV on Day 1; ≥60 years old – 250 mg/m^2 IV, Day 1 or
  - Cytarabine (Cycles 5, 7, and 9): <60 years old – 1000 mg/m^2 IV every 12 hours on Days 1, 3, and 5; ≥60 years old – 250 mg/m^2 IV every 12 hours on Days 1, 3, and 5.

- Maintenance (Cycles 10 to 20): ICLUSIG 30 mg (or decreased to 15 mg if in MRD-negative CR) or imatinib 600 mg once daily in combination with:
  - Vincristine: 1.4 mg/m^2 IV on Day 1 of each cycle; capped at 2 mg and
  - Prednisone: <60 years old – 200 mg orally on Days 1 to 5; ≥60 to 69 years old – 100 mg orally on Days 1 to 5; ≥70 years old – 50 mg orally on Days 1 to 5.

Following combination therapy, patients continued to receive ICLUSIG or imatinib as single-agent therapy until relapse from CR, progressive disease (PD), hematopoietic stem cell transplantation (HSCT), start of alternative therapy, or unacceptable toxicity.

The demographics and baseline disease characteristics of the randomized population are described in Table 11.

Table 11: Demographic and Disease Characteristics for PhALLCON
Patient Characteristics at Entry | ICLUSIG 30 mg → 15 mg with Chemotherapy (N = 164) | Imatinib 600 mg with Chemotherapy (N = 81)
Age (years)
Median, years (range) | 54 (19 to 82) | 52 (19 to 75)
Age Category, n (%)
18 to <45 years | 58 (35%) | 29 (36%)
45 to <60 years | 45 (27%) | 22 (27%)
≥60 years | 61 (37%) | 30 (37%)
Sex, n (%)
Female | 90 (55%) | 43 (53%)
Race, n (%)
White | 104 (63%) | 62 (77%)
Not reported | 28 (17%) | 2 (3%)
Asian | 20 (12%) | 11 (14%)
Black or African American | 9 (5%) | 4 (5%)
ECOG Performance Status, n (%)
0 | 72 (44%) | 33 (41%)
1 | 85 (52%) | 43 (53%)
2 | 7 (4%) | 5 (6%)
Baseline BCR::ABL1 Dominant Variant
p190 | 114 (70%) | 53 (65%)
p210 | 40 (24%) | 25 (31%)
Undetermined/not tested | 10 (6%) | 3 (4%)
Prephase Therapy [Per protocol, patients were allowed to receive one cycle of optional prephase therapy excluding TKI prior to randomization.] | 74 (45%) | 41 (51%)
Comorbidities, n (%)
Hypertension | 58 (35%) | 30 (37%)
Diabetes | 39 (24%) | 24 (30%)
Dyslipidemia | 29 (18%) | 23 (28%)

Among 244 treated patients, 96% completed induction (96% ICLUSIG, 95% imatinib), 84% received at least one cycle of consolidation (89% ICLUSIG, 75% imatinib), and 31% initiated maintenance (36% ICLUSIG, 21% imatinib). After completing combination therapy, 21% of patients received ICLUSIG and 9% received imatinib as single-agent therapy. The overall rate of HSCT was 34% (56/164) in the ICLUSIG arm versus 48% (39/81) in the imatinib arm.

Efficacy was based on the MRD-negative CR rate at the end of induction. The analysis population for MRD-negative CR included 232 randomized patients who had a baseline BCR::ABL1 dominant variant of p190 or p210 as determined by central laboratory tests (154 patients in the ICLUSIG arm and 78 in the imatinib arm). Efficacy results are summarized in Table 12.

Table 12: Efficacy Results in Patients with Ph+ ALL with Baseline BCR::ABL1 Dominant Variant of p190 or p210 in PhALLCON
 | ICLUSIG 30 mg → 15 mg with Chemotherapy (N = 154) | Imatinib 600 mg with Chemotherapy (N = 78)
MRD-negative CR [MRD-negative CR is defined as ≤0.01% BCR::ABL1/ABL1 or undetectable BCR::ABL1 transcripts in cDNA with ≥10,000 ABL1 transcripts, and meeting criteria for CR] at End of Induction
Achieved at the end of induction % (n/N) | 30% (46/154) | 12% (9/78)
Risk difference (95% CI) [Difference, 95% CI and two-sided p-value are based on Cochran-Mantel-Haenszel (CMH) method stratified by the randomization stratification factor.] | 0.18 (0.08, 0.28)
p-value | 0.0004
CR [CR is defined as no circulating blasts and <5% blasts in the bone marrow with normal maturation of all cellular components; no evidence of extramedullary disease (i.e., CNS involvement, lymphadenopathy, splenomegaly, skin/gum infiltration, testicular mass); and hematologic recovery of absolute neutrophil count >1.0 × 10^9/L and platelets >100 × 10^9/L for at least 4 weeks.] at End of Induction % (n/N) | 79% (122/154) | 63% (49/78)
MRD: minimal residual disease; CR: complete remission (complete response); BCR::ABL1: breakpoint cluster region-Abelson.

The median duration of follow-up for overall survival was 20.4 months (95% CI: 18.4, 23.9) in the ICLUSIG arm and 18.1 months (95% CI: 13.9, 24.3) in the imatinib arm.

In the subset of patients who did not receive prephase therapy, MRD-negative CR at the end of induction was achieved by 31% of patients in the ICLUSIG arm compared to 16% of patients in the imatinib arm and CR at the end of induction was achieved by 84% and 61%, respectively.

Chronic Phase (CP) CML

The efficacy of ICLUSIG was evaluated in OPTIC (NCT02467270), a dose-optimization trial. Eligible patients had CP-CML whose disease was considered to be resistant or resistant/intolerant to at least 2 prior kinase inhibitors or who have the T315I mutation. T315I mutation testing was performed on peripheral blood by Sanger Sequencing of the p190 or p210 BCR::ABL region. Resistance in CP-CML while on a prior kinase inhibitor was defined as failure to achieve either a complete hematologic response (by 3 months), a minor cytogenetic response (by 6 months), or a major cytogenetic response (by 12 months), or development of a new BCR::ABL1 kinase domain mutation or new clonal evolution. Patients were required to have >1% BCR::ABL1IS (by real-time polymerase chain reaction) at trial entry. Patients received one of three starting dosages: 45 mg orally once daily, 30 mg orally once daily, or 15 mg orally once daily. Patients who received a starting dose of 45 mg or 30 mg had a dose reduction to 15 mg once daily upon achieving ≤1% BCR::ABL1IS. The major efficacy outcome measure was ≤1% BCR::ABL1IS at 12 months. Only the efficacy results for the recommended starting dose of 45 mg are described below.

The median duration of follow-up for the 45 mg cohort (N=94) was 72.9 months (range: 0.5 months to 106.3 months).

A total of 282 patients received ICLUSIG: 94 received a starting dose of 45 mg, 94 received a starting dose of 30 mg, and 94 received a starting dose of 15 mg. Baseline demographic characteristics are described in Table 13 for patients who received a starting dose of 45 mg.

Table 13: Demographic and Disease Characteristics for OPTIC
Patient Characteristics at Entry | ICLUSIG 45 mg → 15 mg (N = 94)
Age
Median years (range) | 46 (19 to 81)
Sex, n (%)
Male | 50 (53%)
Race, n (%)
White | 73 (78%)
Asian | 16 (17%)
Other/Unknown | 4 (4%)
Black or African American | 1 (1%)
ECOG Performance Status, n (%)
ECOG 0 or 1 | 93 (99%)
Disease History
Median time from diagnosis to first dose, years (range) | 5.5 (1 to 21)
Resistant to Prior Kinase Inhibitor, n (%) | 92 (98%)
Presence of one or more BCR::ABL kinase domain mutations, n (%) | 41 (44%)
Number of Prior Kinase Inhibitors, n (%)
1 | 1 (1%)
2 | 43 (46%)
≥3 | 50 (53%)
T315I mutation at baseline | 25 (27%)
Comorbidities
Hypertension | 29 (31%)
Diabetes | 5 (5%)
Hypercholesterolemia | 3 (3%)
History of ischemic heart disease | 3 (3%)

Efficacy results are summarized in Table 14.

Table 14: Efficacy Results in Patients with CP-CML Who Received ICLUSIG at Starting Dose of 45 mg in OPTIC
 | ICLUSIG 45 mg → 15 mg (N = 93) [ITT population (N=93) defined as patients who had the b2a2/b3a2 (p210) transcript.]
Molecular Response at 12 months [Primary endpoint was ≤1% BCR::ABL1IS rate at 12 months. Defined as a ≤1% ratio of BCR::ABL to ABL transcripts on the International Scale (IS) (i.e., ≤1% BCR::ABLIS; patients must have the b2a2/b3a2 (p210) transcript), in peripheral blood measured by quantitative reverse transcriptase polymerase chain reaction (qRT PCR).]
Overall ≤1% BCR::ABL1IS Rate
% (n/N) | 44% (41/93)
(95% CI) [95% CI is calculated using the binomial exact (Clopper-Pearson) method.] | (34%, 55%)
Patients with T315I mutation
% (n/N) | 44% (11/25)
(95% CI) | (24%, 65%)
Patients without T315I mutation
% (n/N) | 44% (29/66) [Of the 93 patients, two patients did not have a baseline mutation assessment and were excluded from the response by mutation analysis.]
(95% CI) | (32%, 57%)
Cytogenetic Response by 12 months
Major (MCyR) [Secondary endpoint was MCyR by 12 months which combines both complete (no detectable Ph+ cells) and partial (1% to 35% Ph+ cells in at least 20 metaphases) cytogenetic responses.]
% (n/N) | 48% (44/91) [Analysis is based on ITT cytogenetic population (N=91) defined as patients who had a cytogenetic assessment at baseline with at least 20 metaphases examined. One patient who had a complete cytogenetic response at baseline was excluded from the analysis.]
(95% CI) | (38%, 59%)
Patients with T315I mutation
% (n/N) | 52% (13/25)
(95% CI) | (31%, 72%)
Patients without T315I mutation
% (n/N) | 46% (30/65) [Of the 91 patients, one patient did not have a baseline mutation assessment and was excluded from the response by mutation analysis.]
(95% CI) | (34%, 59%)

The rate of molecular response (≤1% BCR::ABL1IS) by 60 months was 60.2% (95% CI 49.5, 70.0). In patients with T3151 mutation, it was 64.0% (95% CI 42.5, 82.0) and in patients without T3151 mutation, it was 59.1% (95% CI, 46.3, 71.0).

Of the 45 patients who had a dose reduction to 15 mg after achieving ≤1% BCR::ABL1IS, 25 patients (56%) maintained their response at the reduced dose for at least one year. Of these 25 patients, 16 patients (64%) maintained response for greater than 60 months. With a minimum follow-up of 60 months, median duration of molecular response (≤1% BCR::ABL1IS) was not reached.

Chronic Phase (CP), Accelerated Phase (AP), Blast Phase (BP) CML and Philadelphia Chromosome-Positive Acute Lymphoblastic Leukemia (Ph+ ALL)

The efficacy of ICLUSIG was evaluated in PACE (NCT01207440), a single-arm, open-label, international, multicenter trial. Eligible patients had CML and Ph+ ALL whose disease was considered to be resistant or intolerant to a prior kinase inhibitor. Patients were assigned to one of six cohorts based on disease phase (CP-CML, AP-CML, or BP-CML/Ph+ ALL), resistance or intolerance (R/I) to prior kinase inhibitors, and the presence of the T315I mutation. T315I mutation testing was performed on peripheral blood by Sanger Sequencing of the p190 or p210 BCR::ABL region.

Resistance in CP-CML while on a prior kinase inhibitor was defined as failure to achieve either a complete hematologic response (by 3 months), a minor cytogenetic response (by 6 months), or a major cytogenetic response (by 12 months). Patients with CP-CML who experienced a loss of response or development of a kinase domain mutation in the absence of a complete cytogenetic response or progression to AP-CML or BP-CML at any time on a prior kinase inhibitor were also considered resistant.

Resistance in AP-CML, BP-CML, and Ph+ ALL was defined as failure to achieve either a major hematologic response (by 3 months in AP-CML, and by 1 month in BP-CML and Ph+ ALL), loss of major hematologic response (at any time), or development of a kinase domain mutation in the absence of a complete major hematologic response while on a prior kinase inhibitor. Intolerance was defined as the discontinuation of a prior kinase inhibitor due to toxicities despite optimal management in the absence of a complete cytogenetic response in patients with CP-CML or major hematologic response for patients with AP-CML, BP-CML, or Ph+ ALL.

Patients were administered a starting dose of ICLUSIG 45 mg orally once daily.

The major efficacy outcome measure for patients with CP-CML was major cytogenetic response (MCyR), which included complete and partial cytogenetic responses (CCyR and PCyR). The major efficacy outcome measure for patients with AP-CML, BP-CML, and Ph+ ALL was major hematologic response (MaHR), defined as either a complete hematologic response (CHR) or no evidence of leukemia (NEL).

The trial enrolled 449 patients, of which 444 were eligible for efficacy analysis: 267 patients with CP-CML (R/I Cohort: N=203, T315I: N=64), 83 patients with AP-CML, 62 patients with BP-CML, and 32 patients with Ph+ ALL. Five patients were not eligible for efficacy analysis due to lack of confirmation of T315I mutation status, and these patients had not received prior dasatinib or nilotinib.

At study completion, the median duration of follow-up for the trial (all cohorts) was 40.5 months (range: 0.1 months to 79.5 months). The median duration of treatment was 35 months for patients with CP-CML, 21.1 months for patients with AP-CML, 3.2 months for patients with BP-CML and 2.9 months for patients with Ph+ ALL. Baseline demographic characteristics are described in Table 15.

Table 15: Demographic and Disease Characteristics for PACE
Patient Characteristics at Entry | Efficacy Population (N = 444)
Age
Median, years (range) | 59 (18 to 94)
Sex, n (%)
Male | 236 (53%)
Race, n (%)
White | 349 (79%)
Asian | 57 (13%)
Black or African American | 25 (6%)
Other/Unknown | 13 (3%)
ECOG Performance Status, n (%)
ECOG = 0 or 1 | 409 (92%)
Disease History
Median time from diagnosis to first dose, years (range) | 6.1 (0.3 to 29)
Resistant to Prior Kinase Inhibitor, n (%) | 374 (88%)
Presence of one or more BCR::ABL kinase domain mutations [Of the patients with one or more BCR::ABL kinase domain mutations detected at entry, 37 unique mutations were detected.] , n (%) | 244 (55%)
Number of Prior Kinase Inhibitor, n (%)
1 | 29 (7%)
2 | 166 (37%)
≥3 | 249 (56%)
T315I mutation at baseline | 128 (29%)
Comorbidities
Hypertension | 159 (35%)
Diabetes | 57 (13%)
Hypercholesterolemia | 100 (22%)
History of ischemic disease | 67 (15%)

Efficacy results are summarized in Table 16 and Table 17.

Table 16: Efficacy of ICLUSIG in Patients with Resistant or Intolerant CP-CML in PACE
 | Overall (N = 267) | Cohort
 | Overall (N = 267) | R/I Cohort (N = 203) | T315I Cohort (N = 64)
Cytogenetic Response
Major [Primary endpoint for CP-CML cohorts was MCyR by 12 months, which combines both complete (no detectable Ph+ cells) and partial (1% to 35% Ph+ cells in at least 20 metaphases) cytogenetic responses.] (MCyR) (95% CI) | 55% (49%, 62%) | 51% (44%, 58%) | 70% (58%, 81%)
Complete (CCyR) (95% CI) | 46% (40%, 52%) | 40% (33%, 47%) | 66% (53%, 77%)
Major Molecular Response [Secondary endpoint for CP-CML cohorts was MMR (proportion of patients who met the criteria for MMR at least once after the initiation of study treatment) measured in peripheral blood. Defined as a ≤0.1% ratio of BCR::ABL to ABL transcripts on the International Scale (IS) (i.e., ≤0.1% BCR::ABLIS; patients must have the b2a2/b3a2 (p210) transcript), in peripheral blood measured by quantitative reverse transcriptase polymerase chain reaction (qRT PCR).] (95% CI) | 40% (35%, 47%) | 35% (28%, 42%) | 58% (45%, 70%)

In patients with CP-CML who achieved MCyR or MMR, the median time to response was 3 months (range: 1.8 to 12.3 months) and 6 months (range: 2 to 60.2 months), respectively. With a minimum follow-up of 60 months, the median durations of MCyR (range: 1 day to 70.1 months) and MMR (range: 1 day to 67.8 months) had not yet been reached.

Table 17: Efficacy of ICLUSIG in Patients with Resistant or Intolerant Advanced Disease (includes R/I and T315I Cohorts) in PACE
 | AP-CML Overall (N = 83) | BP-CML Overall (N = 62) | Ph+ ALL Overall (N = 32)
Hematologic Response
Major [Primary endpoint for patients with AP-CML, BP-CML, and Ph+ ALL was MaHR by 6 months, which combines complete hematologic responses and no evidence of leukemia.] (MaHR) | 57% | 31% | 41%
(95% CI) | (45%, 68%) | (20%, 44%) | (24%, 59%)
Complete [CHR: WBC ≤ institutional ULN, ANC ≥1000/mm^3, platelets ≥100,000/mm^3, no blasts or promyelocytes in peripheral blood, bone marrow blasts ≤5%, <5% myelocytes plus metamyelocytes in peripheral blood, basophils <5% in peripheral blood, no extramedullary involvement (including no hepatomegaly or splenomegaly) .] (CHR) | 51% | 21% | 34%
(95% CI) | (39%, 62%) | (12%, 33%) | (19%, 53%)

The median time to MaHR in patients with AP-CML, BP-CML, and Ph+ ALL was 0.8 months (range: 0.4 to 6.3 months), 1.0 month (range: 0.4 to 4 months), and 0.7 months (range: 0.4 to 6 months), respectively. The median duration of MaHR for patients with AP-CML, BP-CML, and Ph+ ALL was 14 months (range: 1.3 to 74.3 months), 6.5 months (range: 1.9 to 64.7 months), and 3.5 months (range: 1.9 to 13.7 months), respectively.

16 HOW SUPPLIED/STORAGE AND HANDLING

ICLUSIG tablets are available in the following configurations.

Strength | NDC Number | Description | Presentation
10 mg | 63020-536-30 | oval, white to off-white, biconvex film-coated tablets with debossed "NZ" on one side and plain on the other side | 30 tablets in a wide-mouth white high density polyethylene (HDPE) bottle with a desiccant canister and induction sealed child resistant closure.
15 mg | 63020-535-30 | round, white, biconvex film-coated tablets with debossed "A5" on one side and plain on the other side | 30 tablets in a wide-mouth white high density polyethylene (HDPE) bottle with a desiccant canister and induction sealed child resistant closure.
15 mg | 63020-535-60 | round, white, biconvex film-coated tablets with debossed "A5" on one side and plain on the other side | 60 tablets in a wide-mouth white high density polyethylene (HDPE) bottle with a desiccant canister and induction sealed child resistant closure.
30 mg | 63020-533-30 | round, white, biconvex film-coated tablets with debossed "C7" on one side and plain on the other side | 30 tablets in a wide-mouth white high density polyethylene (HDPE) bottle with a desiccant canister and induction sealed child resistant closure.
45 mg | 63020-534-30 | round, white, biconvex film-coated tablets with debossed "AP4" on one side and plain on the other side | 30 tablets in a wide-mouth white high density polyethylene (HDPE) bottle with a desiccant canister and induction sealed child resistant closure.

STORAGE AND HANDLING

Store ICLUSIG tablets at 20°C to 25°C (68°F to 77°F); excursions permitted to 15°C to 30°C (59°F to 86°F) [see USP Controlled Room Temperature].

17 PATIENT COUNSELING INFORMATION

Advise the patient to read the FDA-approved patient labeling (Medication Guide).

Arterial Occlusive Events and Venous Thromboembolic Events

Inform patients that serious arterial thromboses (including arterial stenosis sometimes requiring revascularization) and VTEs have occurred. Advise patients to immediately contact their healthcare provider with any symptoms suggestive of a blood clot such as chest pain, shortness of breath, weakness on one side of the body, speech problems, leg pain, or leg swelling [see Warnings and Precautions (5.1, 5.2)].

Heart Failure and Cardiac Arrhythmias

Inform patients of the possibility of heart failure, and abnormally slow or fast heart rates. Advise patients to contact their healthcare provider if they experience symptoms such as shortness of breath, chest pain, palpitations, dizziness, or fainting [see Warnings and Precautions (5.3, 5.12)].

Hepatotoxicity

Inform patients of the possibility of developing liver function abnormalities and serious hepatotoxicity. Advise patients to immediately contact their healthcare provider if signs of liver failure occur, including jaundice, anorexia, bleeding or bruising [see Warnings and Precautions (5.4)].

Hypertension

Inform patients of the possibility of new or worsening of existing hypertension. Advise patients to contact their healthcare provider for elevated blood pressure or if symptoms of hypertension occur including confusion, headache, dizziness, chest pain, or shortness of breath [see Warnings and Precautions (5.5)].

Pancreatitis

Inform patients of the possibility of developing pancreatitis that may be accompanied by nausea, vomiting, abdominal pain, or abdominal discomfort, and to promptly report these symptoms [see Warnings and Precautions (5.6)].

Neuropathy

Inform patients of the possibility of developing peripheral or cranial neuropathy while being treated with ICLUSIG. Advise patients to report symptoms of neuropathy, such as hypoesthesia, hyperesthesia, paresthesia, discomfort, a burning sensation, neuropathic pain, or weakness [see Warnings and Precautions (5.8)].

Ocular Toxicity

Inform patients of the possibility of ocular toxicity while being treated with ICLUSIG. Advise patients to report symptoms of ocular toxicity, such as blurred vision, dry eye, or eye pain [see Warnings and Precautions (5.9)].

Hemorrhage

Inform patients of the possibility of serious bleeding and to immediately contact their healthcare provider with any signs or symptoms suggestive of hemorrhage such as unusual bleeding or easy bruising [see Warnings and Precautions (5.10)].

Fluid Retention

Inform patients of the possibility of developing fluid retention and to contact their healthcare provider for symptoms such as leg swelling, abdominal swelling, weight gain, or shortness of breath [see Warnings and Precautions (5.11)].

Myelosuppression

Inform patients of the possibility of developing low blood cell counts; inform patients to report immediately should fever develop, particularly in association with any suggestion of infection [see Warnings and Precautions (5.13)].

Tumor Lysis Syndrome

Inform patients of the possibility of developing TLS and to immediately contact their healthcare provider for any signs or symptoms associated with TLS [see Warnings and Precautions (5.14)]. Advise patients to be adequately hydrated when taking ICLUSIG to reduce the risk of TLS.

Reversible Posterior Leukoencephalopathy Syndrome (RPLS – also known as Posterior Reversible Encephalopathy Syndrome)

Inform patients of the possibility of developing Reversible Posterior Leukoencephalopathy Syndrome while being treated with ICLUSIG. Advise patients to report symptoms such as seizure, headache, decreased alertness, altered mental functioning, vision loss, and other visual and neurological disturbances [see Warnings and Precautions (5.15)].

Impaired Wound Healing and Gastrointestinal Perforation

Inform patients that impaired wound healing and gastrointestinal fistula or perforation have been reported. Advise patients to inform their healthcare provider of any planned surgical procedure [see Warnings and Precautions (5.16)].

Embryo-Fetal Toxicity

Advise pregnant women and females of reproductive potential of the potential risk to a fetus. Advise females to inform their healthcare provider of a known or suspected pregnancy. Advise females of reproductive potential to use effective contraception during treatment with ICLUSIG and for 3 weeks after the last dose [see Warnings and Precautions (5.17), Use in Specific Populations (8.1, 8.3)].

Lactation

Advise women not to breastfeed during treatment with ICLUSIG and for 1 week after the last dose [see Use in Specific Populations (8.2)].

Infertility

Advise females of reproductive potential of the potential for reduced fertility from ICLUSIG [see Use in Specific Populations (8.3), Nonclinical Toxicology (13.1)].

Instructions for Taking ICLUSIG

Advise patients to take ICLUSIG exactly as prescribed and not to change their dose or to stop taking ICLUSIG unless they are told to do so by their healthcare provider. ICLUSIG may be taken with or without food. ICLUSIG tablets should be swallowed whole. Patients should not cut, crush or dissolve the tablets.

Patients should not take two doses at the same time to make up for a missed dose.

Advise patients not to drink grapefruit juice or eat grapefruit as it may increase the amount of ICLUSIG in their blood and therefore increase their risk of adverse reactions.

Lactose

Inform patients that ICLUSIG tablets contain lactose monohydrate.

Distributed by:
Takeda Pharmaceuticals America, Inc.
Cambridge, MA 02142

ICLUSIG and are registered trademarks of ARIAD Pharmaceuticals, Inc.
TAKEDA and are registered trademarks of Takeda Pharmaceutical Company Limited.

©2025 Takeda Pharmaceuticals U.S.A., Inc. All rights reserved.

ICL348 R12

MEDICATION GUIDE
ICLUSIG® (eye-CLUE-sig)
(ponatinib)
tablets

What is the most important information I should know about ICLUSIG?
ICLUSIG can cause serious side effects, including:
Blood clots or blockage in your blood vessels (arteries and veins). Blood clots or blockage in your blood vessels may lead to heart attack, stroke, or death. A blood clot or blockage in your blood vessels can prevent proper blood flow to your heart, brain, bowels (intestines), legs, eyes, and other parts of your body. You may need emergency surgery or treatment in a hospital. Get medical help right away if you get any of the following symptoms:

- chest pain or pressure
- pain in your arms, legs, back, neck or jaw
- shortness of breath
- numbness or weakness on one side of your body

- leg swelling
- trouble talking
- headache
- dizziness
- severe stomach area pain
- decreased vision or loss of vision

Blood clots or blockage in your blood vessels can happen in people with or without risk factors for heart and blood vessel disease, including people 50 years of age or younger. The most common risk factors for these problems are a history of high blood pressure (hypertension), high cholesterol, and heart disease. Blood clots or blockages in your blood vessels happen more often in people as they get older, and in people with a history of decreased blood flow, high blood pressure, diabetes, or high cholesterol.
Heart problems. ICLUSIG can cause heart problems, including heart failure which can be serious and may lead to death. Heart failure means your heart does not pump blood well enough. ICLUSIG can also cause irregular, slow, or fast heartbeats and heart attack. Your healthcare provider will check you for heart problems during your treatment with ICLUSIG. Get medical help right away if you get any of the following symptoms: shortness of breath, chest pain, fast or irregular heartbeats, dizziness, or feel faint.
Liver problems. ICLUSIG can cause liver problems, including liver failure, which can be severe and may lead to death. Your healthcare provider will do blood tests before and during your treatment with ICLUSIG to check for liver problems. Get medical help right away if you get any of these symptoms of liver problems during treatment:

- yellowing of your skin or the white part of your eyes
- dark "tea-colored" urine
- sleepiness
- loss of appetite
- bleeding or bruising

See "What are the possible side effects of ICLUSIG?" for information about side effects.

What is ICLUSIG?
ICLUSIG is a prescription medicine used to treat adults who have:

- Philadelphia Chromosome-Positive Acute Lymphoblastic Leukemia (Ph+ ALL)
  - in combination with chemotherapy in newly diagnosed Ph+ ALL
  - alone in adults with Ph+ ALL who cannot receive any other kinase inhibitor medicines or who have a specific type of abnormal gene (T315I-positive) Ph+ ALL
- Chronic Myeloid Leukemia (CML)
- chronic phase CML who did not tolerate or no longer benefit from treatment with at least 2 prior kinase inhibitor medicines
- accelerated phase or blast phase CML who cannot receive any other kinase inhibitor medicines
- a specific type of abnormal gene (T315I-positive) chronic phase, accelerated phase, or blast phase CML

ICLUSIG is not for use to treat people with newly diagnosed chronic phase CML.
It is not known if ICLUSIG is safe and effective in children.

Before you take ICLUSIG, tell your healthcare provider about all of your medical conditions, including if you:

- have a history of blood clots in your blood vessels (arteries or veins)
- have heart problems, including heart failure, irregular heartbeats, and QT prolongation

- have diabetes
- have a history of high cholesterol
- have liver problems
- have had inflammation of your pancreas (pancreatitis)
- have high blood pressure

- have bleeding problems
- plan to have surgery or have had a recent surgery. You should stop taking ICLUSIG at least 1 week before planned surgery. See "What are the possible side effects of ICLUSIG?"
- are lactose (milk sugar) intolerant. ICLUSIG tablets contain lactose.
- eat grapefruit or drink grapefruit juice. See "How should I take ICLUSIG?"

- are pregnant or plan to become pregnant. ICLUSIG can harm your unborn baby.
  - Your healthcare provider will do a pregnancy test before you start taking ICLUSIG.
  - For females who can become pregnant:
    - Use an effective form of birth control during treatment and for 3 weeks after your last dose of ICLUSIG.
    - Tell your healthcare provider right away if you become pregnant or think you might be pregnant during treatment with ICLUSIG.
    - ICLUSIG may affect your ability to have children. Tell your healthcare provider if this is a concern for you.
- are breastfeeding or plan to breastfeed. It is not known if ICLUSIG passes into your breast milk. Do not breastfeed during treatment and for 1 week after your last dose of ICLUSIG.

Tell your healthcare provider about all the medicines you take, including prescription medicines and over-the-counter medicines, vitamins, and herbal supplements. ICLUSIG and other medicines may affect each other causing side effects.
Know the medicines you take. Keep a list of them to show your healthcare provider and pharmacist when you get a new medicine.

How should I take ICLUSIG?

- Take ICLUSIG exactly as your healthcare provider tells you to take it.
- Do not change your dose or stop taking ICLUSIG unless your healthcare provider tells you.
- Swallow ICLUSIG tablets whole. Do not crush, break, cut, chew or dissolve ICLUSIG tablets.
- Take ICLUSIG with or without food.
- Do not eat grapefruit or drink grapefruit juice during treatment with ICLUSIG.
- If you miss a dose of ICLUSIG, take your next dose at your regularly scheduled time the next day. Do not take 2 doses at the same time to make up for a missed dose.
- If you take too much ICLUSIG, call your healthcare provider or go to the nearest hospital emergency room right away.

What are the possible side effects of ICLUSIG?
ICLUSIG may cause serious side effects, including:

- See "What is the most important information I should know about ICLUSIG?"
- High blood pressure (hypertension). High blood pressure is common during treatment with ICLUSIG and can also be serious or severe. ICLUSIG can cause new or worsening high blood pressure. Your blood pressure should be checked regularly, and any high blood pressure should be treated during treatment with ICLUSIG. Tell your healthcare provider right away if you get confusion, headaches, dizziness, chest pain or shortness of breath.
- Inflammation of the pancreas (pancreatitis). Pancreatitis is common during treatment with ICLUSIG and can also be serious or severe. Tell your healthcare provider right away if you get any of the following symptoms: sudden stomach-area pain or discomfort, nausea, and vomiting. Your healthcare provider should do blood tests to check for pancreatitis during treatment with ICLUSIG.
- Neuropathy. ICLUSIG may cause damage to the nerves in your arms, brain, hands, legs, or feet (neuropathy). Tell your healthcare provider right away if you get any of these symptoms during treatment with ICLUSIG:
  - muscle weakness, tingling, burning, pain, discomfort or loss of feeling in your hands and feet
  - double vision and other problems with eyesight, trouble moving the eye, drooping of part of the face, sagging or drooping eyelids, or change in taste
- Eye problems. Serious eye problems that can lead to blindness or blurred vision may happen with ICLUSIG. Tell your healthcare provider right away if you get any of the following symptoms: bleeding in the eye, perceived flashes of light, light sensitivity, floaters, blurred vision, dry, inflamed, swollen, or itchy eyes, or eye pain. Your healthcare provider will monitor your vision before and during your treatment with ICLUSIG.
- Bleeding. Bleeding is common during treatment with ICLUSIG and can also be serious and may lead to death. Tell your healthcare provider right away if you get any signs of bleeding during treatment with ICLUSIG including:

- vomiting blood or if your vomit looks like coffee-grounds
- pink or brown urine
- red or black (looks like tar) stools
- coughing up blood or blood clots
- unusual bleeding or bruising of your skin
- menstrual bleeding that is heavier than normal

- unusual vaginal bleeding
- nose bleeds that happen often
- drowsiness or difficulty being awakened
- confusion
- headache
- change in speech

- Fluid retention. Your body may hold too much fluid (fluid retention) which can be serious and may lead to death. Tell your healthcare provider right away if you get any of these symptoms during treatment with ICLUSIG:
  - swelling of your hands, ankles, feet, face, or all over your body
  - weight gain
  - shortness of breath and cough
- Irregular heartbeat. ICLUSIG may cause an irregular heartbeat. Tell your healthcare provider right away if you experience loss of consciousness, fainting, dizziness, chest pain or palpitations.
- Low blood cell counts. ICLUSIG may cause low blood cell counts, which can be severe. Your healthcare provider will check your blood counts regularly during treatment with ICLUSIG. Tell your healthcare provider right away if you have a fever or any signs of an infection while taking ICLUSIG.
- Tumor Lysis Syndrome (TLS). TLS is caused by a fast breakdown of cancer cells. TLS can cause you to have kidney failure and the need for dialysis treatment, and an abnormal heartbeat.
  Your healthcare provider may do blood tests to check for TLS. Drink plenty of water during treatment with ICLUSIG to help reduce your risk of getting TLS. Call your healthcare provider or get emergency help right away if you get any of the following symptoms during treatment with ICLUSIG:

- nausea and vomiting
- weakness
- swelling

- shortness of breath
- muscle cramps
- seizures

- Reversible Posterior Leukoencephalopathy Syndrome (RPLS – also known as Posterior Reversible Encephalopathy Syndrome). ICLUSIG may trigger a condition called RPLS. Call your healthcare provider right away if you get headaches, seizures, confusion, changes in vision or problems thinking.
- Wound healing problems. Wound healing problems have happened in some people who take ICLUSIG. Tell your healthcare provider if you plan to have any surgery before or during treatment with ICLUSIG.
  - You should stop taking ICLUSIG at least 1 week before planned surgery.
  - Your healthcare provider should tell you when you may start taking ICLUSIG again after surgery.
- A tear in your stomach or intestinal wall (perforation). Tell your healthcare provider right away if you get:
  - severe pain in your stomach-area (abdomen)
  - swelling of the abdomen
  - high fever

The most common side effects of ICLUSIG when given alone include:

- skin rash
- joint pain
- stomach-area (abdomen) pain
- tiredness
- headache
- constipation
- high blood pressure
- dry skin

- liver problems
- swelling of your hands, ankles, feet, face, or all over your body (fluid retention and edema)
- fever
- increase in lipase levels (a blood test done to check your pancreas)
- nausea
- bleeding

- low hemoglobin in the blood (anemia)
- blood clots or blockage in blood vessels (arteries)
- irregular heartbeat
- low blood platelet counts
- low blood levels of white blood cells

The most common side effects of ICLUSIG when given with chemotherapy include:

- liver problems
- joint pain
- skin rash
- headache
- fever
- stomach-area (abdomen) pain
- constipation
- tiredness
- nausea

- mouth sores
- high blood pressure
- increase in lipase levels (a blood test done to check your pancreas)
- numbness or tingling (pins and needles), pain, or weakness in the hands or feet
- bleeding
- fever due to low white blood cell counts (febrile neutropenia)

- swelling of your hands, ankles, feet, face, or all over your body (fluid retention and edema)
- vomiting
- irregular heartbeat
- low blood platelet counts
- low blood levels of white blood cells
- low hemoglobin in the blood (anemia)
- changes in liver function tests

Your healthcare provider may change your dose, temporarily stop, or permanently stop treatment with ICLUSIG if you have certain side effects.
Tell your healthcare provider if you have any side effect that bothers you or that does not go away.
These are not all of the possible side effects of ICLUSIG. For more information, ask your healthcare provider or pharmacist.
Call your doctor for medical advice about side effects. You may report side effects to FDA at 1-800-FDA-1088.

How should I store ICLUSIG?
Store ICLUSIG at room temperature between 68°F to 77°F (20°C to 25°C).
Keep ICLUSIG and all medicines out of the reach of children.

General information about the safe and effective use of ICLUSIG
Medicines are sometimes prescribed for purposes other than those listed in a Medication Guide. Do not use ICLUSIG for a condition for which it was not prescribed. Do not give ICLUSIG to other people, even if they have the same symptoms you have. It may harm them. You can ask your healthcare provider or pharmacist for information about ICLUSIG that is written for health professionals.

What are the ingredients in ICLUSIG?
Active ingredient: ponatinib
Inactive ingredients: lactose monohydrate, microcrystalline cellulose, sodium starch glycolate (type B), colloidal silicon dioxide and magnesium stearate. The tablet coating consists of talc, polyethylene glycol, polyvinyl alcohol and titanium dioxide.
Distributed by: Takeda Pharmaceuticals America, Inc.
Cambridge, MA 02142
ICLUSIG and are registered trademarks of ARIAD Pharmaceuticals, Inc.
TAKEDA and are registered trademarks of Takeda Pharmaceutical Company Limited.
©2025 Takeda Pharmaceuticals U.S.A., Inc. All rights reserved.
For more information, go to www.iclusig.com or call 1-844-817-6468. ICL348 R12

This Medication Guide has been approved by the U.S. Food and Drug Administration.

Revised: 10/2025

PRINCIPAL DISPLAY PANEL - 15 mg Tablet Bottle Label

NDC 63020-535-30

ICLUSIG®
(ponatinib) tablets

15 mg

Each tablet contains 15 mg ponatinib
equivalent to 16.03 mg ponatinib HCl

Dispense Attached Medication Guide

30 tablets
Rx only

Takeda

PRINCIPAL DISPLAY PANEL - 45 mg Tablet Bottle Label

NDC 63020-534-30

ICLUSIG®
(ponatinib) tablets

45 mg

Each tablet contains 45 mg ponatinib
equivalent to 48.08 mg ponatinib HCl

Dispense Attached Medication Guide

Takeda

PRINCIPAL DISPLAY PANEL - 30 mg Tablet Bottle Label

NDC 63020-533-30

ICLUSIG®
(ponatinib) tablets

30 mg

Each tablet contains 30 mg ponatinib
equivalent to 32.05 mg ponatinib HCl

Dispense Attached Medication Guide

Takeda

PRINCIPAL DISPLAY PANEL - 10 mg Tablet Bottle Label

NDC 63020-536-30

ICLUSIG®
(ponatinib) tablets

10 mg

Each tablet contains 10 mg ponatinib
equivalent to 10.68 mg ponatinib HCl

Dispense Attached Medication Guide

30 tablets
Rx only

Takeda